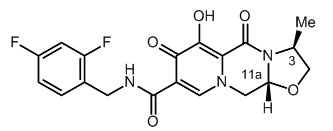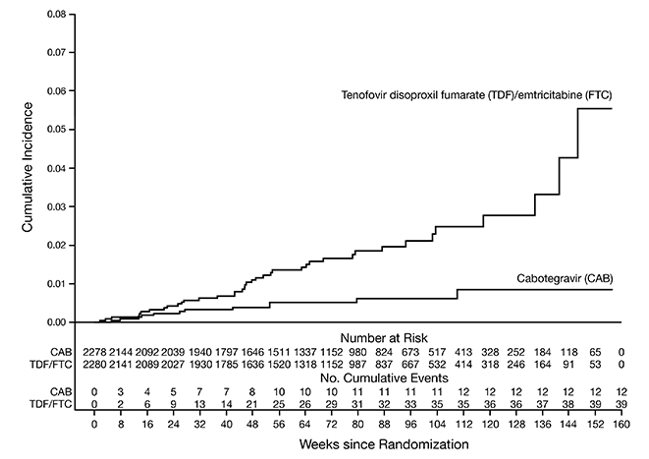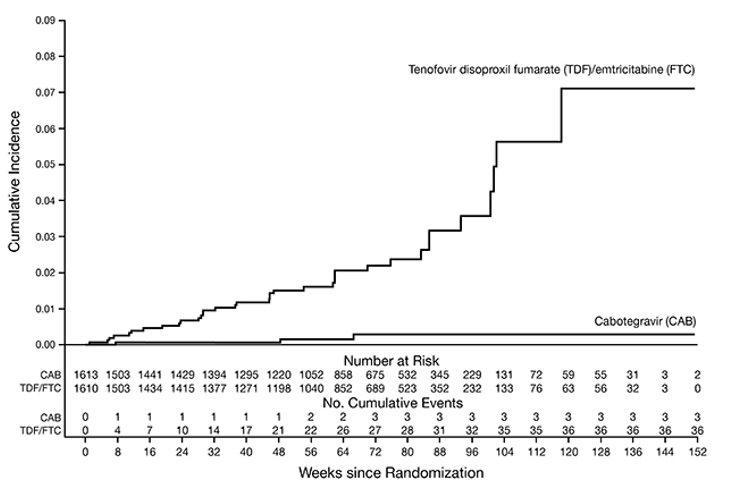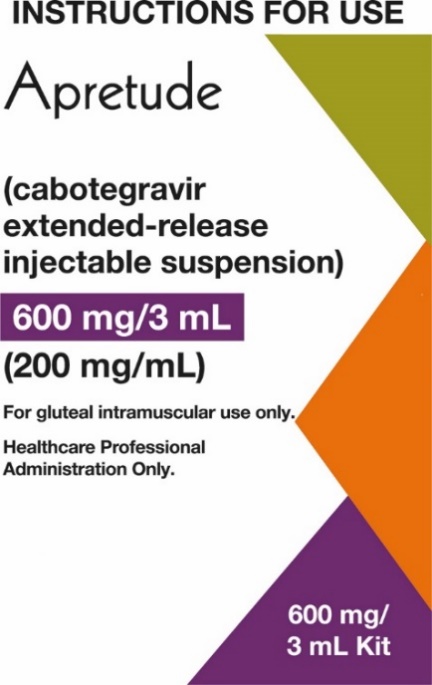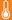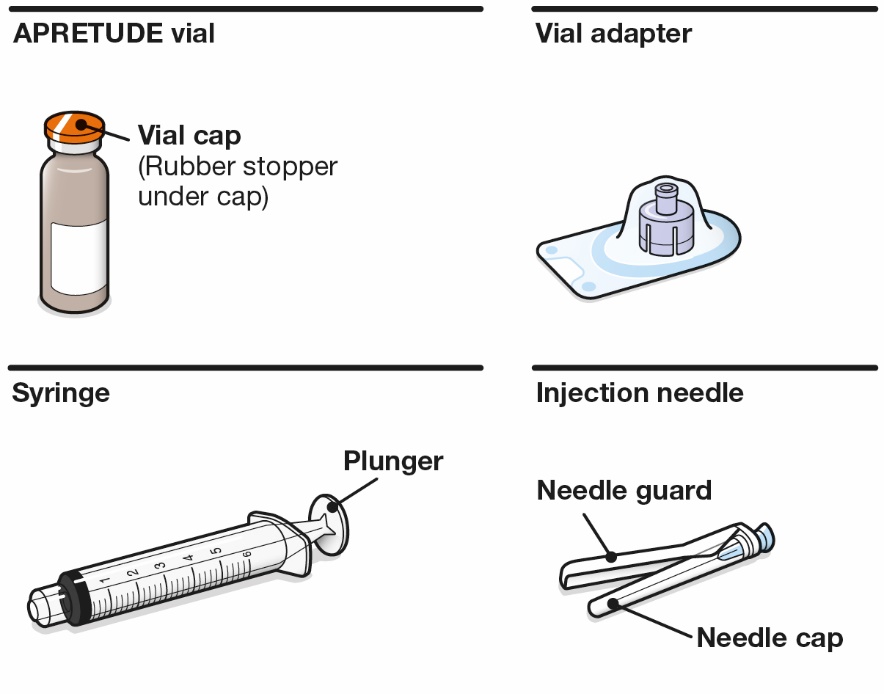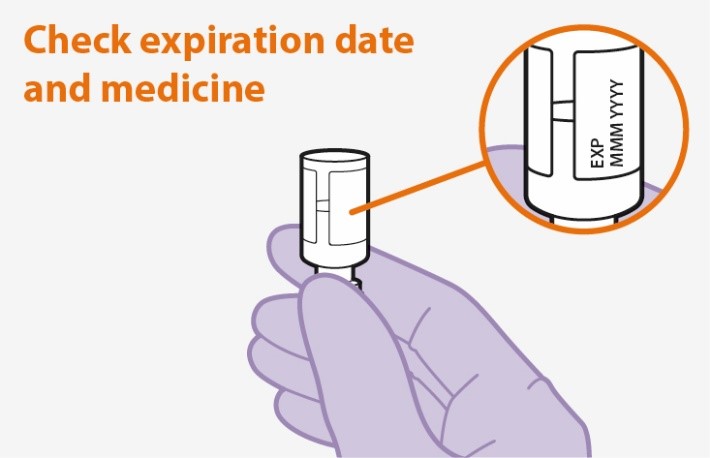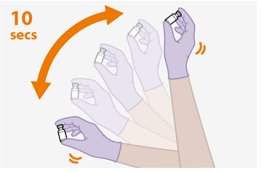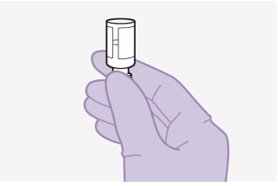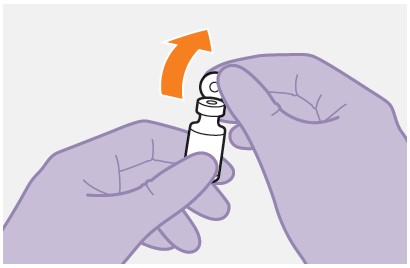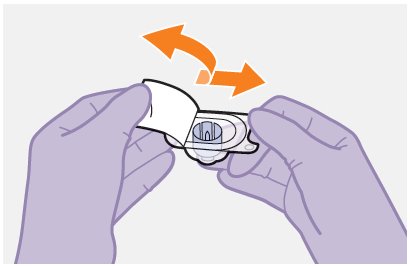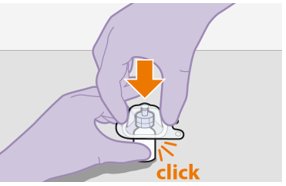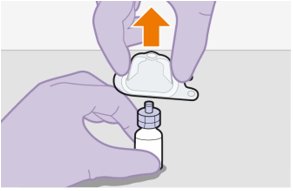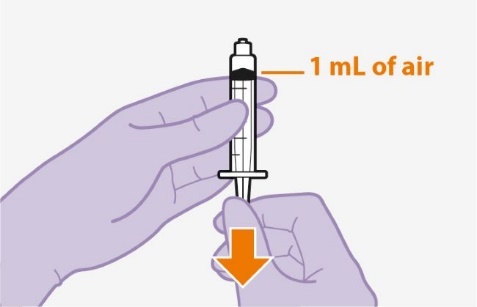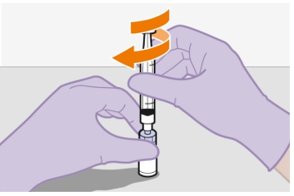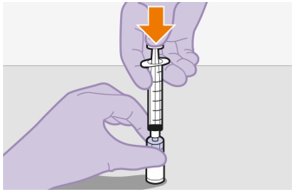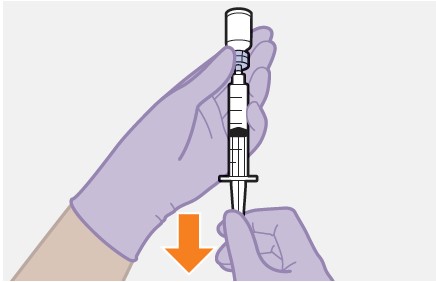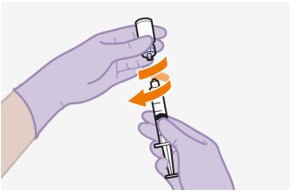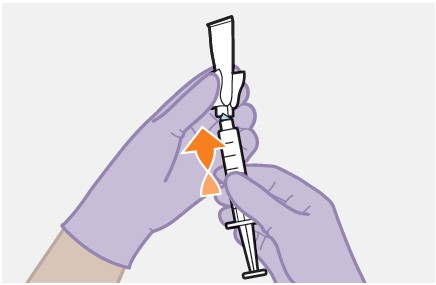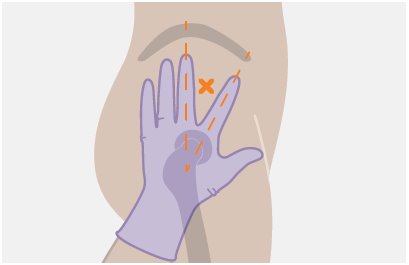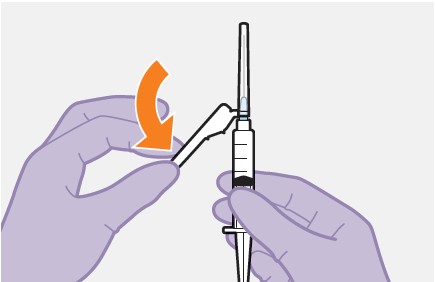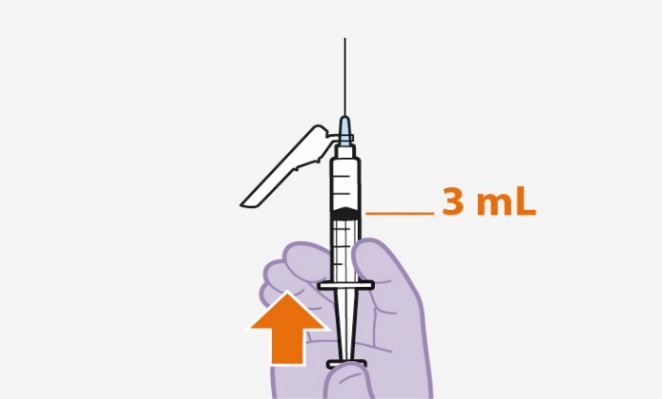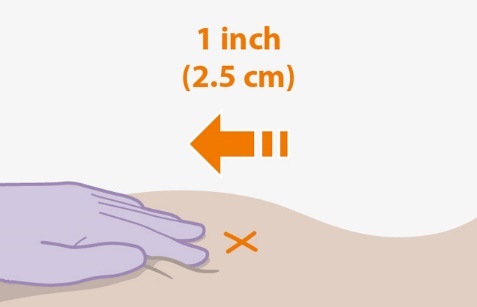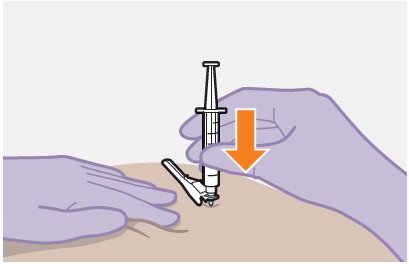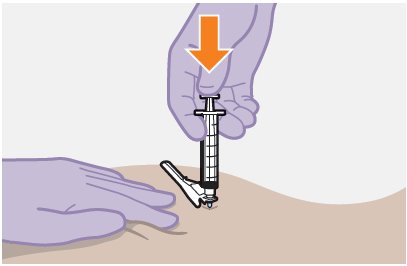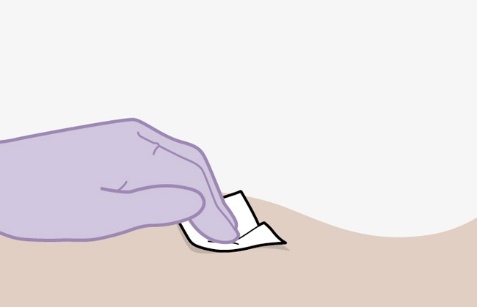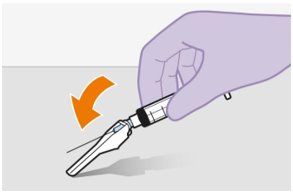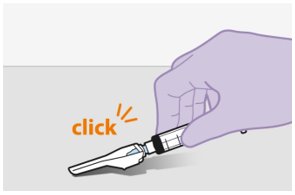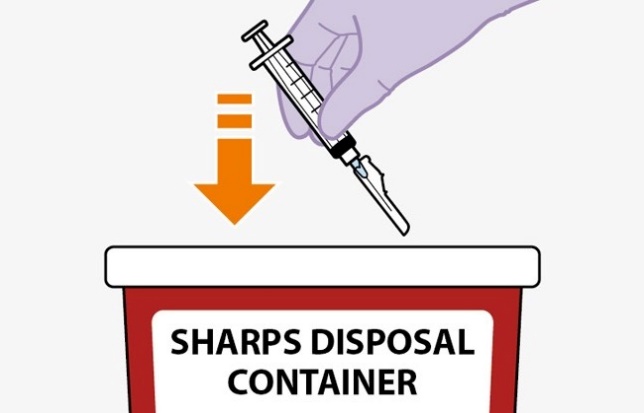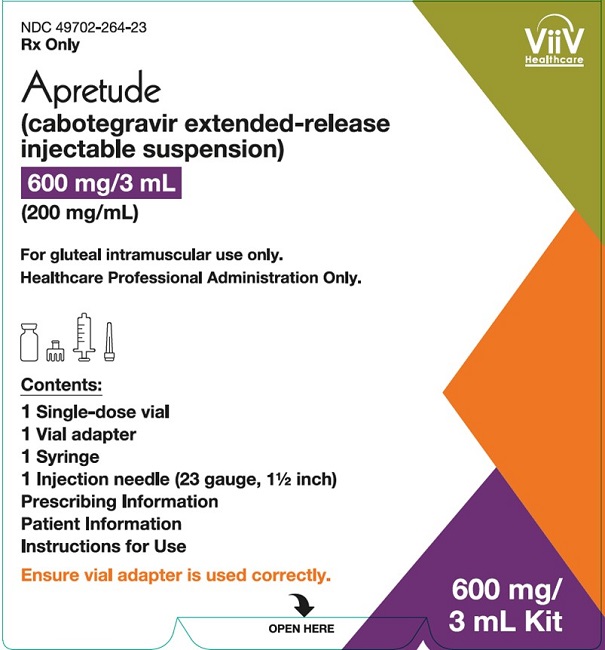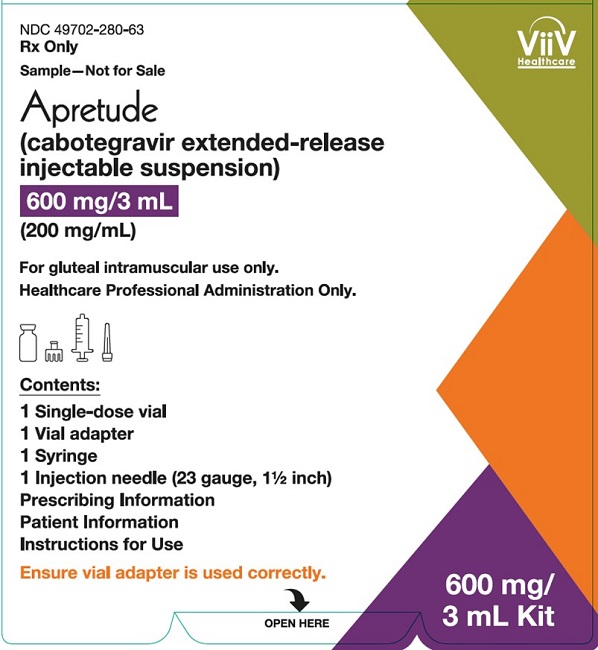 DRUG LABEL: Apretude
NDC: 49702-264 | Form: KIT | Route: INTRAMUSCULAR
Manufacturer: ViiV Healthcare Company
Category: prescription | Type: HUMAN PRESCRIPTION DRUG LABEL
Date: 20250411

ACTIVE INGREDIENTS: CABOTEGRAVIR 200 mg/1 mL
INACTIVE INGREDIENTS: MANNITOL; POLYETHYLENE GLYCOL 3350; POLYSORBATE 20; WATER

HIGHLIGHTS OF PRESCRIBING INFORMATION

These highlights do not include all the information needed to use APRETUDE safely and effectively. See full prescribing information for APRETUDE.
APRETUDE (cabotegravir extended-release injectable suspension), for intramuscular use
Initial U.S. Approval: 2021

RECENT MAJOR CHANGES

Warnings and Precautions, Hypersensitivity Reactions (5.4) | 4/2025

WARNING: RISK OF DRUG RESISTANCE WITH USE OF APRETUDE FOR HIV-1 PRE‑EXPOSURE PROPHYLAXIS (PrEP) IN UNDIAGNOSED HIV-1 INFECTION

See full prescribing information for complete boxed warning.

Individuals must be tested for HIV-1 infection prior to initiating APRETUDE or oral cabotegravir, and with each subsequent injection of APRETUDE, using a test approved or cleared by the FDA for the diagnosis of acute or primary HIV-1 infection. Drug-resistant HIV-1 variants have been identified with use of APRETUDE for HIV-1 PrEP by individuals with undiagnosed HIV-1 infection. Do not initiate APRETUDE for HIV-1 PrEP unless negative infection status is confirmed. Individuals who acquire HIV-1 while receiving APRETUDE for PrEP must transition to a complete HIV-1 treatment regimen. (2.2, 4, 5.1)

1 INDICATIONS AND USAGE

APRETUDE is an HIV-1 integrase strand transfer inhibitor (INSTI) indicated for PrEP to reduce the risk of sexually acquired HIV-1 infection in adults and adolescents weighing at least 35 kg who are at risk for HIV-1 acquisition. Individuals must have a negative HIV-1 test prior to initiating APRETUDE (with or without an oral lead-in with oral cabotegravir) for HIV-1 PrEP. (1)

2 DOSAGE AND ADMINISTRATION

- HIV-1 Screening: Screen all individuals for HIV-1 infection immediately prior to initiating APRETUDE for HIV-1 PrEP and prior to each injection while taking APRETUDE. (2.2)
- Prior to initiating APRETUDE, an oral lead-in dosing may be used for approximately 1 month with the recommended dosage to assess the tolerability of APRETUDE. (2.4)
- For gluteal intramuscular injection only. (2.5, 2.7)
- Recommended Dosing Schedule: Initiate APRETUDE with a single 600-mg (3-mL) injection given 1 month apart for 2 consecutive months on the last day of an oral lead-in if used or within 3 days and continue with the injections every 2 months thereafter. (2.5)

3 DOSAGE FORMS AND STRENGTHS

Injection: Single-dose vial of 600 mg/3 mL (200 mg/mL) of cabotegravir extended-release injectable suspension. (3)

4 CONTRAINDICATIONS

- Unknown or positive HIV-1 status. (4)
- Previous hypersensitivity reaction to cabotegravir. (4)
- Coadministration with drugs where significant decreases in cabotegravir plasma concentrations may occur. (4)

5 WARNINGS AND PRECAUTIONS

- Comprehensive management to reduce the risk of HIV-1 acquisition. (5.1)
- Potential risk of developing resistance to APRETUDE if an individual acquires HIV-1 either before or while taking APRETUDE or following discontinuation of APRETUDE. Reassess risk of HIV-1 acquisition and test before each injection to confirm HIV-1 negative status. (5.2)
- Residual concentrations of cabotegravir may remain in the systemic circulation of individuals up to 12 months or longer. (5.3)
- Serious or severe hypersensitivity reactions have been reported with cabotegravir and include Stevens-Johnson syndrome (SJS)/toxic epidermal necrolysis (TEN). Discontinue APRETUDE immediately if signs or symptoms of hypersensitivity reactions develop. (5.4)
- Hepatotoxicity has been reported in individuals receiving cabotegravir. Clinical and laboratory monitoring should be considered. Discontinue APRETUDE if hepatotoxicity is suspected. (5.5)
- Depressive disorders have been reported with APRETUDE. Prompt evaluation is recommended for depressive symptoms. (5.6)

6 ADVERSE REACTIONS

The most common adverse reactions (all grades) observed in at least 1% of participants receiving APRETUDE were injection site reactions, diarrhea, headache, pyrexia, fatigue, sleep disorders, nausea, dizziness, flatulence, abdominal pain, vomiting, myalgia, rash, decreased appetite, somnolence, back pain, and upper respiratory tract infection. (6.1)

To report SUSPECTED ADVERSE REACTIONS, contact ViiV Healthcare at 1-877-844-8872 or FDA at 1-800-FDA-1088 or www.fda.gov/medwatch.

7 DRUG INTERACTIONS

- Refer to the full prescribing information for important drug interactions with APRETUDE. (4, 5.7, 7)
- Drugs that induce uridine diphosphate glucuronosyltransferase (UGT)1A1 may significantly decrease plasma concentrations of cabotegravir. (4, 7.2, 7.3)

8 USE IN SPECIFIC POPULATIONS

- Lactation: Assess the benefit-risk of using APRETUDE to the infant while breastfeeding due to the potential for adverse reactions and residual concentrations in the systemic circulation for up to 12 months or longer after discontinuation. (8.2)
- Pediatrics: Not recommended in individuals weighing <35 kg. (8.4)

FULL PRESCRIBING INFORMATION

WARNING: RISK OF DRUG RESISTANCE WITH USE OF APRETUDE FOR HIV-1 PRE‑EXPOSURE PROPHYLAXIS (PrEP) IN UNDIAGNOSED HIV-1 INFECTION

Individuals must be tested for HIV-1 infection prior to initiating APRETUDE or oral cabotegravir, and with each subsequent injection of APRETUDE, using a test approved or cleared by the FDA for the diagnosis of acute or primary HIV-1 infection. Drug-resistant HIV-1 variants have been identified with use of APRETUDE by individuals with undiagnosed HIV-1 infection. Do not initiate APRETUDE for HIV-1 PrEP unless negative infection status is confirmed. Individuals who acquire HIV-1 while receiving APRETUDE for PrEP must transition to a complete HIV-1 treatment regimen [see Dosage and Administration (2.2), Contraindications (4), Warnings and Precautions (5.1)].

1 INDICATIONS AND USAGE

APRETUDE is indicated for pre‑exposure prophylaxis (PrEP) to reduce the risk of sexually acquired HIV-1 infection in adults and adolescents weighing at least 35 kg who are at risk for HIV-1 acquisition. Individuals must have a negative HIV-1 test prior to initiating APRETUDE (with or without an oral lead-in with oral cabotegravir) for HIV-1 PrEP [see Dosage and Administration (2.2, 2.4), Contraindications (4), Warnings and Precautions (5.1)].

2 DOSAGE AND ADMINISTRATION

2.1 Dosage and Administration Overview

- APRETUDE contains cabotegravir extended-release injectable suspension in a single-dose vial [see Dosage Forms and Strengths (3)].
- APRETUDE must be administered by a healthcare provider by gluteal intramuscular injection [see Dosage and Administration (2.7)].
- APRETUDE may be initiated with oral cabotegravir prior to the intramuscular injections or the patient may proceed directly to injection of APRETUDE without an oral lead-in [see Dosage and Administration (2.4)].

2.2 HIV-1 Screening for Individuals Receiving APRETUDE for HIV-1 Pre-Exposure Prophylaxis

Individuals must be tested for HIV-1 infection prior to initiating APRETUDE or oral cabotegravir, and with each subsequent injection of APRETUDE, using a test approved or cleared by the FDA for the diagnosis of acute or primary HIV-1 infection. If an antigen/antibody-specific test is used and provides negative results, then such negative results should be confirmed using an RNA-specific assay, even if the results of the RNA-assay are available after APRETUDE or oral cabotegravir administration [see Contraindications (4), Warnings and Precautions (5.1)].

2.3 Adherence to APRETUDE

Prior to starting APRETUDE, healthcare providers should carefully select individuals who agree to the required injection dosing and testing schedule and counsel individuals about the importance of adherence to scheduled dosing visits to help reduce the risk of acquiring HIV-1 infection and development of resistance [see Dosage and Administration (2.1), Warnings and Precautions (5.1, 5.3), Microbiology (12.4)].

2.4 Optional Oral Lead-In Dosing to Assess Tolerability of APRETUDE

The healthcare provider and individual may decide to use an oral lead-in with oral cabotegravir prior to the initiation of APRETUDE to assess the tolerability of cabotegravir or the healthcare provider and individual may proceed directly to injection of APRETUDE without the use of an oral lead-in [see Dosage and Administration (2.5)].

No safety and efficacy data are available for use of APRETUDE without an oral lead-in [see Warnings and Precautions (5.3), Adverse Reactions (6.1)]. However, in HIV-1 treatment clinical trials, data show that an oral lead-in is not needed to ensure adequate plasma cabotegravir exposure upon initiation of injections and that the safety and efficacy results of CABENUVA (cabotegravir extended-release injectable suspension; rilpivirine extended-release injectable suspension) were similar when administered with and without an oral lead-in.

2.5 Gluteal Intramuscular Injection Dosing with APRETUDE

Initiation Injections

If an oral lead-in is used, initiation injections should be administered on the last day of oral lead‑in or within 3 days thereafter. The recommended initiation injection doses of APRETUDE in individuals is a single 600‑mg (3-mL) intramuscular injection of APRETUDE given 1 month apart for 2 consecutive months (Table 1 and Table 2). Individuals may be given the second APRETUDE initiation injection up to 7 days before or after the date the individual is scheduled to receive the injections.

Continuation Injections

After the 2 initiation injection doses given consecutively 1 month apart, the recommended continuation injection dose of APRETUDE is a single 600-mg (3-mL) intramuscular injection of APRETUDE every 2 months (Table 2). Individuals may be given APRETUDE up to 7 days before or after the date the individual is scheduled to receive the injections.

Table 1. Recommended Dosing Schedule (with Oral Lead-In) for Pre-Exposure Prophylaxis in Adults and Adolescents Weighing at Least 35 kg
Oral Lead-In (at Least 28 Days); (Month Prior to Starting Injections) | Intramuscular (Gluteal) Initiation Injection (Month 1 and Month 2) | Intramuscular (Gluteal) Continuation Injection (Month 4 and Every 2 Months Onwards)
Oral cabotegravir 30 mg by mouth once daily for 28 days | APRETUDEa; 600-mg (3 mL) | APRETUDEb; 600-mg (3 mL)
a Should be administered on the last day of oral lead-in or within 3 days thereafter.
b Individuals may be given APRETUDE up to 7 days before or after the date the individual is scheduled to receive the injections.

Table 2. Recommended Dosing Schedule (Direct to Injection) for Pre-Exposure Prophylaxis in Adults and Adolescents Weighing at Least 35 kg
Intramuscular (Gluteal) Initiation Injection (Month 1 and Month 2) | Intramuscular (Gluteal) Continuation Injection (Month 4 and Every 2 Months Onwards)
APRETUDEa | APRETUDEa
600-mg (3 mL) | 600-mg (3 mL)
a Individuals may be given APRETUDE up to 7 days before or after the date the individual is scheduled to receive the injections.

2.6 Recommended Dosing Schedule for Missed Injections

Adherence to the injection dosing schedule is strongly recommended [see Dosage and Administration (2.3)]. Individuals who miss a scheduled injection visit should be clinically reassessed to ensure resumption of APRETUDE remains appropriate [see Dosage and Administration (2.2), Warnings and Precautions (5.1, 5.2)]. Refer to Table 3 for dosing recommendations after missed injections.

Planned Missed Injections

If an individual plans to miss a scheduled every-2-month continuation injection visit by more than 7 days, take daily oral cabotegravir for up to 2 months to replace 1 missed scheduled every-2-month injection. The recommended oral daily dose is one 30-mg tablet of oral cabotegravir. The first dose of oral cabotegravir (or alternative oral PrEP regimen) should be taken approximately 2 months after the last injection dose of APRETUDE. Restart injection with APRETUDE on the day oral cabotegravir dosing completes or within 3 days, thereafter, as recommended in Table 3. For oral PrEP durations greater than 2 months, an alternative regimen to oral cabotegravir is recommended.

Unplanned Missed Injections

If a scheduled injection visit is missed or delayed by more than 7 days and oral dosing has not been taken in the interim, clinically reassess the individual to determine if resumption of injection dosing remains appropriate [see Warnings and Precautions (5.1)]. If the injection dosing schedule will be continued, see Table 3 for dosing recommendations.

Table 3. Injection Dosing Recommendations after Missed Injections
Time since Last Injection | Recommendation
If second injection is missed and time since first injection is:
Less than or equal to 2 months | Administer 600-mg (3-mL) gluteal intramuscular injection of APRETUDE as soon as possible, then continue to follow the every-2-month injection dosing schedule.
Greater than 2 months | Restart with 600-mg (3-mL) gluteal intramuscular injection of APRETUDE, followed by a second 600-mg (3-mL) initiation injection dose 1 month later. Then continue to follow the every-2-month injection dosing schedule thereafter.
If third or subsequent injection is missed and time since prior injection is:
Less than or equal to 3 months | Administer 600-mg (3-mL) intramuscular injection of APRETUDE as soon as possible, then continue with the every-2-month injection dosing schedule.
Greater than 3 months | Restart with 600-mg (3-mL) gluteal intramuscular injection of APRETUDE, followed by the second 600-mg (3-mL) initiation injection dose 1 month later. Then continue with the every-2-month injection dosing schedule thereafter.

2.7 Administration Instructions

Refer to the Instructions for Use for complete administration instructions with illustrations. Carefully follow these instructions and ensure that the vial adaptor is used correctly when preparing the suspension for injection to avoid leakage.

APRETUDE is a suspension for gluteal intramuscular injection that does not need further dilution or reconstitution.

The ventrogluteal site is recommended for injection. A dorsogluteal approach (upper outer quadrant) is acceptable, if preferred by the healthcare professional. Do not administer by any other route or anatomical site. Consider the body mass index (BMI) of the individual to ensure that the needle length is sufficient to reach the gluteus muscle. Longer needle lengths (not included in the dosing kit) may be required for individuals with higher BMI (e.g., >30 kg/m^2) to ensure that the injection is administered intramuscularly as opposed to subcutaneously.

If the pack has been stored in the refrigerator, the vial should be brought to room temperature prior to administration (not to exceed 30°C [86°F]).

Parenteral drug products should be inspected visually for particulate matter and discoloration prior to administration whenever solution and container permit. The APRETUDE vial has a brown tint to the glass that may limit visual inspection. Discard the vial if the medicine exhibits particulate matter or discoloration.

Shake the vial vigorously so that the suspension looks uniform before injecting. Small air bubbles are expected and acceptable.

Once the suspension has been drawn into the syringe, the injection should be administered as soon as possible, but may remain in the syringe for up to 2 hours. The filled syringe should not be placed in the refrigerator. If the medicine remains in the syringe for more than 2 hours, the filled syringe and needle must be discarded [see How Supplied/Storage and Handling (16)].

3 DOSAGE FORMS AND STRENGTHS

Injection: Single-dose vial containing 600 mg/3 mL (200 mg/mL) of cabotegravir extended‑release injectable suspension.

4 CONTRAINDICATIONS

APRETUDE is contraindicated in individuals:

- with unknown or positive HIV-1 status [see Warnings and Precautions (5.1, 5.2)].
- with previous hypersensitivity reaction to cabotegravir [see Warnings and Precautions (5.4)].
- receiving the following coadministered drugs for which significant decreases in cabotegravir plasma concentrations may occur due to uridine diphosphate glucuronosyltransferase (UGT)1A1 enzyme induction, which may result in reduced effectiveness [see Drug Interactions (7.2, 7.3), Clinical Pharmacology (12.3)]:
  - Anticonvulsants: Carbamazepine, oxcarbazepine, phenobarbital, phenytoin
  - Antimycobacterials: Rifampin, rifapentine

5 WARNINGS AND PRECAUTIONS

5.1 Comprehensive Management to Reduce the Risk of HIV-1 Infection

Use APRETUDE for HIV-1 PrEP to reduce the risk of HIV-1 infection as part of a comprehensive prevention strategy including adherence to the administration schedule and safer sex practices, including condoms, to reduce the risk of sexually transmitted infections (STIs). APRETUDE is not always effective in preventing HIV-1 acquisition [see Clinical Studies (14.1)]. The time from initiation of APRETUDE for HIV-1 PrEP to maximal protection against HIV-1 infection is unknown.

Risk for HIV-1 acquisition includes behavioral, biological, or epidemiologic factors including, but not limited to, condomless sex, past or current STIs, self-identified HIV risk, having sexual partners of unknown HIV-1 viremic status, or sexual activity in a high prevalence area or network.

Counsel individuals on the use of other prevention measures (e.g., consistent and correct condom use; knowledge of partner(s)’ HIV-1 status, including viral suppression status; regular testing for STIs that can facilitate HIV-1 transmission). Inform individuals about and support their efforts in reducing sexual risk behavior.

Use APRETUDE to reduce the risk of acquiring HIV-1 only in individuals confirmed to be HIV‑1 negative [see Contraindications (4)]. HIV-1 resistance substitutions may emerge in individuals with undiagnosed HIV‑1 infection who are taking only APRETUDE, because APRETUDE alone does not constitute a complete regimen for HIV-1 treatment [see Microbiology (12.4)]; therefore, care should be taken to minimize the risk of initiating or continuing APRETUDE before confirming the individual is HIV-1 negative.

- Prior to initiating APRETUDE for HIV-1 PrEP, ask seronegative individuals about recent (in past month) potential exposure events (e.g., condomless sex or condom breaking during sex with a partner of unknown HIV-1 status or unknown viremic status, a recent STI), and evaluate for current or recent signs or symptoms consistent with acute HIV-1 infection (e.g., fever, fatigue, myalgia, skin rash).
- If recent (<1 month) exposures to HIV-1 are suspected or clinical symptoms consistent with acute HIV-1 infection are present, use a test approved or cleared by the FDA as an aid in the diagnosis of acute or primary HIV-1 infection.

When using APRETUDE for HIV-1 PrEP, HIV-1 testing should be repeated prior to each injection and upon diagnosis of any other STIs [see Dosage and Administration (2.2, 2.5)].

- If an HIV-1 test indicates possible HIV-1 infection, or if symptoms consistent with acute HIV-1 infection develop following an exposure event, additional HIV testing to determine HIV status is needed. If an individual has confirmed HIV-1 infection, then the individual must be transitioned to a complete HIV-1 treatment regimen.

Counsel individuals without HIV-1 to strictly adhere to the recommended dosing and testing schedule for APRETUDE in order to reduce the risk of HIV-1 acquisition and the potential development of resistance [see Dosage and Administration (2.3, 2.5), Microbiology (12.4)]. Some individuals, such as adolescents, may benefit from frequent visits and counseling to support adherence to the dosing and testing schedule [see Use in Specific Populations (8.4), Microbiology (12.4), Clinical Studies (14)].

5.2 Potential Risk of Resistance with APRETUDE

There is a potential risk of developing resistance to APRETUDE if an individual acquires HIV-1 either before or while taking APRETUDE or following discontinuation of APRETUDE [see Warnings and Precautions (5.1, 5.3)].

To minimize this risk, it is essential to clinically reassess individuals for risk of HIV-1 acquisition and to test before each injection to confirm HIV-1 negative status. Individuals who are confirmed to have HIV-1 infection must transition to a complete HIV-1 treatment regimen.

Alternative forms of PrEP should be considered following discontinuation of APRETUDE for those individuals at continuing risk of HIV-1 acquisition and initiated within 2 months of the final injection of APRETUDE.

5.3 Long-Acting Properties and Potential Associated Risks with APRETUDE

Residual concentrations of cabotegravir may remain in the systemic circulation of individuals for prolonged periods (up to 12 months or longer). It is important to carefully select individuals who agree to the required every-2-month injection dosing schedule because non-adherence to every‑2-monthly injections or missed doses could lead to HIV-1 acquisition and development of resistance.

Healthcare providers should take the prolonged-release characteristics of cabotegravir into consideration when APRETUDE is prescribed [see Dosage and Administration (2.3), Warnings and Precautions (5.1, 5.2), Drug Interactions (7.1), Use in Specific Populations (8.1, 8.2), Overdosage (10)].

5.4 Hypersensitivity Reactions

Serious or severe hypersensitivity reactions have been reported with cabotegravir and include Stevens-Johnson syndrome (SJS)/toxic epidermal necrolysis (TEN) [see Adverse Reactions (6.2)]. Administration of cabotegravir oral lead-in dosing was used in clinical studies to help identify participants who may be at risk of a hypersensitivity reaction. Remain vigilant and discontinue APRETUDE if a hypersensitivity reaction is suspected [see Dosage and Administration (2.4), Contraindications (4), Adverse Reactions (6)].

Discontinue APRETUDE immediately if signs or symptoms of hypersensitivity reactions develop (including, but not limited to, severe rash, or rash accompanied by fever, general malaise, fatigue, muscle or joint aches, blisters, mucosal involvement [oral blisters or lesions], conjunctivitis, facial edema, hepatitis, eosinophilia, angioedema, difficulty breathing). Clinical status, including liver transaminases, should be monitored and appropriate therapy initiated. For information regarding the long-acting properties of APRETUDE [see Warnings and Precautions (5.3)].

5.5 Hepatotoxicity

Hepatotoxicity has been reported in a limited number of individuals receiving cabotegravir with or without known pre-existing hepatic disease or identifiable risk factors [see Adverse Reactions (6.1)].

Clinical and laboratory monitoring should be considered and APRETUDE should be discontinued if hepatotoxicity is suspected and individuals managed as clinically indicated. For information regarding the long-acting properties of APRETUDE [see Warnings and Precautions (5.3)].

5.6 Depressive Disorders

Depressive disorders (including depression, depressed mood, major depression, persistent depressive disorder, suicidal ideation, suicide attempt) have been reported with APRETUDE [see Adverse Reactions (6.1)]. Promptly evaluate individuals with depressive symptoms to assess whether the symptoms are related to APRETUDE and to determine whether the risks of continued therapy outweigh the benefits.

5.7 Risk of Reduced Drug Concentration of APRETUDE Due to Drug Interactions

The concomitant use of APRETUDE and other drugs may result in reduced drug concentration of APRETUDE [see Contraindications (4), Drug Interactions (7.2, 7.3)].

See Table 8 for steps to prevent or manage these possible and known significant drug interactions, including dosing recommendations. Consider the potential for drug interactions prior to and during use of, and after discontinuation of APRETUDE; review concomitant medications during use of APRETUDE [see Drug Interactions (7.3, 7.4)].

6 ADVERSE REACTIONS

The following adverse reactions are described below and in other sections of the labeling:

- Hypersensitivity reactions [see Warnings and Precautions (5.4)]
- Hepatotoxicity [see Warnings and Precautions (5.5)]
- Depressive disorders [see Warnings and Precautions (5.6)]

6.1 Clinical Trials Experience

Because clinical trials are conducted under widely varying conditions, adverse reaction rates observed in the clinical trials of a drug cannot be directly compared with rates in the clinical trials of another drug and may not reflect rates observed in practice.

Clinical Trials Experience in Adults

The safety assessment of APRETUDE is based on the analysis of data from 2 international, multicenter, double-blind trials, HPTN 083 and HPTN 084 [see Clinical Studies (14.1)].

Adverse reactions were reported while on blinded study product following exposure to APRETUDE extended-release injectable suspension and oral cabotegravir tablets as oral lead-in. The median time on blinded study product in HPTN 083 was 65 weeks and 2 days (range: 1 day to 156 weeks and 1 day), with a total exposure on cabotegravir of 3,231 person‑years. The median time on blinded study product in HPTN 084 was 64 weeks and 1 day (range: 1 day to 153 weeks and 1 day), with a total exposure on cabotegravir of 2,009 person‑years.

The most common adverse reactions regardless of severity reported in at least 1% of participants in HPTN 083 or HPTN 084 are presented in Table 4.

In HPTN 083, 6% of participants in the group receiving APRETUDE intramuscular injection every 2 months and 4% of participants receiving oral TRUVADA [emtricitabine (FTC) and tenofovir disoproxil fumarate (TDF)] once daily discontinued due to adverse events (all causality). Non-injection-site–associated adverse events leading to discontinuation and occurring in ≥1% of participants were increased alanine aminotransferase with APRETUDE and TRUVADA.

In HPTN 084, 1% of participants receiving APRETUDE and 1% of participants receiving TRUVADA discontinued due to adverse events. The most commonly reported adverse event (all causality) leading to discontinuation was increased alanine aminotransferase (<1%) with APRETUDE and TRUVADA. The side-by-side tabulation is to simplify presentation; direct comparison across trials should not be made due to differing trials.

Table 4. Adverse Drug Reactionsa (All Grades) Reported in at Least 1% of Participants Receiving APRETUDE in Either HPTN 083 or HPTN 084
Adverse Reactions | HPTN 083 |  | HPTN 084
Adverse Reactions | APRETUDE; Every 2 Months; (n = 2,281) | TRUVADA; Once Daily; (n = 2,285) | APRETUDE; Every 2 Months; (n = 1,614) | TRUVADA; Once Daily; (n = 1,610)
Injection site reactionsb | 82% | 35% | 38% | 11%
Diarrhea | 4% | 5% | 4% | 4%
Headache | 4% | 3% | 12% | 13%
Pyrexiac | 4% | <1% | <1% | <1%
Fatigued | 4% | 2% | 3% | 3%
Sleep disorderse | 3% | 3% | 1% | 1%
Nausea | 3% | 5% | 4% | 8%
Dizziness | 2% | 3% | 4% | 6%
Flatulence | 1% | 1% | <1% | <1%
Abdominal painf | 1% | 1% | 2% | 2%
Vomiting | <1% | 1% | 2% | 5%
Myalgia | <1% | <1% | 2% | 1%
Rashg | <1% | <1% | 2% | 1%
Decreased appetite | <1% | <1% | 2% | 4%
Somnolence | <1% | <1% | 2% | 2%
Back pain | <1% | <1% | 1% | <1%
Upper respiratory tract infection | 0 | <1% | 4% | 4%
a Adverse reactions defined as “treatment-related” as assessed by the investigator, with exception of injection site reactions, where all injection site reactions were reported regardless of causality.
b Participants who received injection: HPTN 083, APRETUDE (n = 2,117) and TRUVADA (n = 2,081); HPTN 084, APRETUDE (n = 1,519) and TRUVADA (n = 1,516).
c Pyrexia includes pyrexia, feeling hot, chills, influenza-like illness.
d Fatigue includes fatigue, malaise.
e Sleep disorders includes insomnia, abnormal dreams.
f Abdominal pain includes abdominal pain, upper abdominal pain.
g Rash includes rash, erythema, pruritis, macular, papular, maculopapular.

Injection-Associated Adverse Reactions: Local Injection Site Reactions (ISRs) with APRETUDE: The most frequent adverse reactions associated with the intramuscular administration of APRETUDE in HPTN 083 were ISRs. After 20,286 injections, 8,900 ISRs were reported. Of the 2,117 participants who received at least one injection of APRETUDE, 1,740 (82%) participants experienced at least one ISR, of which a total of 3% of participants discontinued APRETUDE because of ISRs. Among the participants who received APRETUDE and experienced at least one ISR, the maximum severity of reactions was mild (Grade 1) in 41% of participants, moderate (Grade 2) in 56% of participants, and severe (Grade 3) in 3% of participants. The median duration of overall ISR events was 4 days. The proportion of participants reporting ISRs at each visit and the severity of the ISRs decreased over time. The most commonly reported ISRs (all causality and grades) in at least 1% of participants who received APRETUDE and experienced at least one ISR from HPTN 083 are presented in Table 5.

The most frequent adverse reactions associated with the intramuscular administration of APRETUDE in HPTN 084 were ISRs. After 13,068 injections, 1,171 ISRs were reported. Of the 1,519 participants who received at least one injection of APRETUDE, 578 (38%) participants experienced at least one ISR. No participants discontinued APRETUDE because of ISRs. Among the participants who received APRETUDE and experienced at least one ISR, the maximum severity of reactions was mild (Grade 1) in 66% of participants, moderate (Grade 2) in 34% of participants, and severe (Grade 3) in less than 1% of participants. The median duration of overall ISR events was 8 days. The proportion of participants reporting ISRs at each visit and the severity of the ISRs generally decreased over time. The most commonly reported ISRs (all causality and grades) in at least 1% of participants who received APRETUDE and experienced at least one ISR from HPTN 084 are presented in Table 5.

Table 5. Injection Site Reactions (All Grades) Reported in at Least 1% of Participants Who Experienced at Least One Injection Site Reaction (All Causality) with APRETUDE in Either HPTN 083 or HPTN 084
Injection Site Reactions | HPTN 083 |  | HPTN 084
Injection Site Reactions | APRETUDE; (n = 1,740) | TRUVADAa; (n = 724) | APRETUDE; (n = 578) | TRUVADAa; (n = 166)
Pain/tenderness | 98% | 95% | 90% | 87%
Nodules | 15% | 2% | 14% | 2%
Induration | 15% | <1% | 12% | 2%
Swelling | 12% | 1% | 18% | 3%
Bruising | 4% | 4% | 1% | 0
Erythema | 4% | 2% | 5% | 2%
Pruritus | 3% | 3% | 6% | 11%
Warmth | 3% | 1% | <1% | 0
Anesthesia | 1% | 2% | 1% | 2%
Abscess | <1% | 0 | 2% | 3%
Discoloration | <1% | 0 | 1% | 0
a Placebo injectable suspension: intralipid 20% fat emulsion.

Other Injection-Associated Adverse Reactions: In the HPTN 083 clinical trial, an increased incidence of pyrexia (including pyrexia, feeling hot, chills, influenza-like illness) (4%) was reported by participants receiving APRETUDE compared with participants receiving TRUVADA (<1%). There were no differences reported in the incidence of pyrexia between groups in HPTN 084.

Vasovagal or pre-syncopal reactions considered treatment related were reported in <1% of participants after injection with APRETUDE in HPTN 083. None were reported as treatment related by the investigators in HPTN 084.

Less Common Adverse Reactions: The following select adverse reactions (regardless of severity) occurred in <1% of participants receiving APRETUDE in HPTN 083 or HPTN 084.

Hepatobiliary Disorders: Hepatotoxicity.

Investigations: Weight increase (see below).

Psychiatric Disorders: Depression; suicidal ideation, and suicide attempt (these events were observed primarily in participants with a pre‑existing history of depression or other psychiatric illness).

Weight Increase: At the Week 41 and Week 97 timepoints in HPTN 083, participants who received APRETUDE gained a median of 1.2 kg (Interquartile Range [IQR]; -1.0, 3.5; n = 1,623) and 2.1 kg (IQR; -0.9, 5.9; n = 601) in weight from baseline. Those who received TRUVADA gained a median of 0 kg (IQR; -2.1, 2.4; n = 1,611) and 1 kg (IQR; -1.9, 4.0; n = 598) in weight from baseline, respectively.

At the Week 41 and 97 timepoints in HPTN 084, participants who received APRETUDE gained a median of 2 kg (IQR; 0.0, 5.0; n = 1,151) and 4 kg (IQR; 0.0, 8.0; n = 216) in weight from baseline, respectively. Those who received TRUVADA gained a median of 1 kg (IQR; -1.0, 4.0; n = 1,131) and 3 kg (IQR; -1.0, 6.0; n = 218) in weight from baseline, respectively.

Laboratory Abnormalities: Grade 3 or 4 post-baseline maximum toxicity laboratory abnormalities for HPTN 083 or HPTN 084 are summarized in Table 6.

Table 6. Laboratory Abnormalities (Grades 3 to 4) in ≥1% of Participants in Either HPTN 083 or HPTN 084
Laboratory Parameter | HPTN 083 |  | HPTN 084
Laboratory Parameter | APRETUDE; Every 2 Months; (n = 2,281) | TRUVADA; Once Daily; (n = 2,285) | APRETUDE; Every 2 Months; (n = 1,614) | TRUVADA; Once Daily; (n = 1,610)
ALT (≥5.0 x ULN) | 2% | 2% | <1% | 1%
AST (≥5.0 x ULN) | 3% | 3% | <1% | <1%
Creatine phosphokinase (≥10.0 x ULN) | 15% | 14% | 2% | 2%
Lipase (≥3.0 x ULN) | 3% | 3% | <1% | <1%
Creatinine (>1.8 x ULN) or increase to ≥1.5 x baseline) | 3% | 3% | 5% | 4%
ALT = Alanine transaminase, ULN = upper limit of normal, AST = Aspartate aminotransferase.

Serum Lipids: Changes from baseline to Month 15 in total cholesterol, HDL cholesterol, LDL cholesterol, triglycerides, and total cholesterol to HDL ratio in HPTN 083 and HPTN 084 are presented in Table 7.

Table 7. Fasting Lipid Values, Median Change from Baselinea at Week 57, Reported in HPTN 083 and HPTN 084
 | HPTN 083 |  | HPTN 084
 | APRETUDE | TRUVADA | APRETUDE | TRUVADA
Total cholesterol (mg/dL) | +1.0 | -10.0 | +0.2 | -3.9
LDL cholesterol (mg/dL) | +1.0 | -6.0 | -1.1 | -5.0
HDL cholesterol (mg/dL) | -0.2 | -3.0 | -0.8 | -2.6
Triglycerides (mg/dL) | +2.7 | 0.0 | +3.1 | +0.7
Total cholesterol: HDL cholesterol ratio | +0.1 | +0.0 | +0.1 | +0.1
a Nearly 60% of participants with baseline data available had Week 57 data available in both arms of both trials. Within each trial, baseline values were comparable among participants receiving APRETUDE and TRUVADA.

Clinical Trials Experience in Adolescents

In adolescents receiving APRETUDE for HIV-1 PrEP, the safety data were comparable to the safety data reported in adults receiving APRETUDE for HIV-1 PrEP [see Use in Specific Populations (8.4)].

6.2 Postmarketing Experience

The following adverse reactions have been identified during postmarketing use of APRETUDE or cabotegravir-containing regimens. Because these reactions are reported voluntarily from a population of uncertain size, it is not always possible to reliably estimate their frequency or establish a causal relationship to drug exposure.

Immune System Disorders

Hypersensitivity reactions (including angioedema and urticaria) [see Warnings and Precautions (5.4)].

Skin and Subcutaneous Tissue Disorders

Stevens-Johnson syndrome (SJS)/toxic epidermal necrolysis (TEN) [see Warnings and Precautions (5.4)].

7 DRUG INTERACTIONS

7.1 Use of Other Antiretroviral Drugs after Discontinuation of APRETUDE

Residual concentrations of cabotegravir may remain in the systemic circulation of individuals for prolonged periods (up to 12 months or longer). These residual concentrations are not expected to affect the exposures of antiretroviral drugs that are initiated after discontinuation of APRETUDE [see Warnings and Precautions (5.3), Drug Interactions (7.4), Clinical Pharmacology (12.3)].

7.2 Potential for Other Drugs to Affect APRETUDE

Cabotegravir is primarily metabolized by UGT1A1 with some contribution from UGT1A9. Drugs that are strong inducers of UGT1A1 or 1A9 are expected to decrease cabotegravir plasma concentrations; therefore, coadministration of APRETUDE with these drugs is contraindicated [see Contraindications (4)].

7.3 Established and Other Potentially Significant Drug Interactions

Information regarding potential drug interactions with cabotegravir is provided in Table 8. These recommendations are based on either drug interaction trials following oral administration of cabotegravir or predicted interactions due to the expected magnitude of the interaction [see Contraindications (4), Warnings and Precautions (5.7), Clinical Pharmacology (12.3)]. Table 8 includes potentially significant interactions but is not all inclusive.

Table 8. Drug Interactions with APRETUDE
Concomitant Drug Class:; Drug Name | Effect on Concentration | Clinical Comment
Anticonvulsants:; Carbamazepine; Oxcarbazepine; Phenobarbital; Phenytoin | ↓Cabotegravir | Coadministration is contraindicated with APRETUDE due to potential for significant decreases in plasma concentration of APRETUDE.
Antimycobacterials:; Rifampin; Rifapentine | ↓Cabotegravir | Coadministration is contraindicated with APRETUDE due to potential for significant decreases in plasma concentration of APRETUDE.
Antimycobacterial:; Rifabutin | ↓Cabotegravir | When rifabutin is started before or concomitantly with the first initiation injection of APRETUDE, the recommended dosing of APRETUDE is one 600-mg (3-mL) injection, followed 2 weeks later by a second 600‑mg (3-mL) initiation injection and monthly thereafter while on rifabutin. When rifabutin is started at the time of the second initiation injection or later, the recommended dosing schedule of APRETUDE is 600‑mg (3 mL) monthly while on rifabutin.; After stopping rifabutin, the recommended dosing schedule of APRETUDE is 600-mg (3 mL) every 2 months.
↑ = Increase, ↓ = Decrease, ↔ = No change.

7.4 Drugs without Clinically Significant Interactions with Cabotegravir

Based on drug interaction study results, the following drugs can be coadministered with cabotegravir (non-antiretrovirals) or given after discontinuation of cabotegravir (antiretrovirals and non-antiretrovirals) without a dose adjustment: etravirine, midazolam, oral contraceptives containing levonorgestrel and ethinyl estradiol, and rilpivirine [see Clinical Pharmacology (12.3)].

8 USE IN SPECIFIC POPULATIONS

8.1 Pregnancy

Pregnancy Exposure Registry

There is a pregnancy exposure registry that monitors pregnancy outcomes in individuals exposed to APRETUDE during pregnancy. Healthcare providers are encouraged to register individuals by calling the Antiretroviral Pregnancy Registry (APR) at 1-800-258-4263.

Risk Summary

There are insufficient human data on the use of APRETUDE during pregnancy to adequately assess a drug-associated risk of birth defects and miscarriage. Discuss the benefit-risk of using APRETUDE with individuals of childbearing potential or during pregnancy.

Cabotegravir use in pregnant individuals has not been evaluated. APRETUDE should be used during pregnancy only if the expected benefit justifies the potential risk to the fetus.

The APR has been established to monitor for birth defects following prenatal exposure to antiretrovirals. The rate of miscarriage is not reported in the APR. The background rate for major birth defects in a U.S. reference population of the Metropolitan Atlanta Congenital Defects Program (MACDP) is 2.7%. The estimated background rate of miscarriage in clinically recognized pregnancies in the U.S. general population is 15% to 20%. The APR uses the MACDP as the U.S. reference population for birth defects in the general population. The MACDP evaluates mothers and infants from a limited geographic area and does not include outcomes for births that occurred at <20 weeks’ gestation.

In animal reproduction studies with oral cabotegravir, a delay in the onset of parturition and increased stillbirths and neonatal deaths were observed in a rat pre- and postnatal development study at >28 times the exposure at the recommended human dose (RHD). No evidence of adverse developmental outcomes was observed with oral cabotegravir in rats or rabbits (>28 times or similar to the exposure at the RHD, respectively) given during organogenesis (see Data).

Clinical Considerations

Cabotegravir is detected in systemic circulation for up to 12 months or longer after discontinuing injections of APRETUDE; therefore, consideration should be given to the potential for fetal exposure during pregnancy [see Warnings and Precautions (5.3)].

Data

Animal Data: Cabotegravir was administered orally to pregnant rats at 0, 0.5, 5, or 1,000 mg/kg/day from 15 days before cohabitation, during cohabitation, and from Gestation Days 0 to 17. There were no effects on fetal viability when fetuses were delivered by caesarean, although a minor decrease in fetal body weight was observed at 1,000 mg/kg/day (>28 times the exposure in humans at the RHD). No drug-related fetal toxicities were observed at 5 mg/kg/day (approximately 13 times the exposure in humans at the RHD), and no drug-related fetal malformations were observed at any dose.

Cabotegravir was administered orally to pregnant rabbits at 0, 30, 500, or 2,000 mg/kg/day from Gestation Days 7 to 19. No drug-related fetal toxicities were observed at 2,000 mg/kg/day (approximately 0.7 times the exposure in humans at the RHD).

In a rat pre- and postnatal development study, cabotegravir was administered orally to pregnant rats at 0, 0.5, 5, or 1,000 mg/kg/day from Gestation Day 6 to Lactation Day 21. A delay in the onset of parturition and increases in the number of stillbirths and neonatal deaths by Lactation Day 4 were observed at 1,000 mg/kg/day (>28 times the exposure in humans at the RHD); there were no alterations to growth and development of surviving offspring. In a cross-fostering study, similar incidences of stillbirths and early postnatal deaths were observed when rat pups born to cabotegravir-treated mothers were nursed from birth by control mothers. There was no effect on neonatal survival of control pups nursed from birth by cabotegravir-treated mothers. A lower dose of 5 mg/kg/day (13 times the exposure at the RHD) was not associated with delayed parturition or neonatal mortality in rats. Studies in pregnant rats showed that cabotegravir crosses the placenta and can be detected in fetal tissue.

8.2 Lactation

Risk Summary

There are no data on the presence of cabotegravir in human milk. Cabotegravir is present in animal milk (see Data). When a drug is present in animal milk, it is likely that the drug will be present in human milk. It is not known if cabotegravir affects human milk production, or has effects on the breastfed infant. If cabotegravir is present in human milk, residual exposures may remain for 12 months or longer after the last injections have been administered [see Warnings and Precautions (5.3)].

Cabotegravir concentrations may be detectable in systemic circulation for up to 12 months or longer after discontinuing injections of APRETUDE. Breastfeeding should only be considered if the expected benefit justifies the potential risk to the infant, including the potential risk for adverse reaction in the breastfed child, along with the risk of HIV-1 acquisition due to nonadherence and subsequent vertical transmission to the child. Breastfeeding is not recommended if acute HIV-1 infection is suspected to avoid the risk of postnatal transmission of HIV-1 infection.

Data

Animal lactation studies with cabotegravir have not been conducted. However, cabotegravir was detected in the plasma of nursing pups on Lactation Day 10 in the rat pre- and postnatal development study.

8.4 Pediatric Use

The safety and effectiveness of APRETUDE for HIV-1 PrEP in adolescents weighing at least 35 kg who are at risk for HIV-1 acquisition is supported by data from 2 adequate and well-controlled trials of APRETUDE for HIV-1 PrEP in adults with additional safety and pharmacokinetic data from studies in adults with HIV-1 who were administered CABENUVA, and in adolescent participants with HIV-1 who were administered separate components of CABENUVA in addition to their current antiretroviral therapy [see Dosage and Administration (2.5), Adverse Reactions (6.1), Clinical Pharmacology (12.3), Clinical Studies (14.1)].

APRETUDE for HIV-1 PrEP was evaluated in 2 open-label multicenter clinical trials, HPTN 083-01 and HPTN 084-01, in adolescent individuals 12 to less than 18 years of age weighing at least 35 kg who are at risk for HIV-1 acquisition. Sixty-four adolescents were enrolled. Of these, 62 adolescent participants received one or more injections. In adolescents receiving APRETUDE for HIV-1 PrEP, the safety data were comparable to the safety data reported in adults receiving APRETUDE for HIV-1 PrEP.

While using APRETUDE, HIV-1 testing should be conducted prior to initiating APRETUDE (with or without an oral lead-in with oral cabotegravir) and prior to each injection of APRETUDE. Adolescents may benefit from more frequent visits and counseling to support adherence to the dosing and testing schedule [see Dosage and Administration (2.2), Warnings and Precautions (5.1)].

The safety, efficacy, and pharmacokinetics of APRETUDE in pediatric participants younger than 12 years of age or weighing <35 kg have not been established.

8.5 Geriatric Use

No dose adjustment is required in elderly individuals. There are limited data available on the use of APRETUDE in individuals aged 65 years and older. In general, caution should be exercised in administration of APRETUDE in elderly individuals, reflecting greater frequency of decreased hepatic, renal, or cardiac function and of concomitant disease or other drug therapy [see Clinical Pharmacology (12.3)].

8.6 Renal Impairment

Based on studies with oral cabotegravir, no dosage adjustment of APRETUDE is necessary for individuals with mild (creatinine clearance ≥60 to <90 mL/min), moderate (creatinine clearance ≥30 to <60 mL/min) or severe renal impairment (creatinine clearance ≥15 to <30 mL/min) [see Clinical Pharmacology (12.3)]. In individuals with end-stage renal disease not on dialysis, effects on the pharmacokinetics of cabotegravir are unknown. As cabotegravir is >99% protein bound, dialysis is not expected to alter exposures of cabotegravir.

8.7 Hepatic Impairment

Based on studies with oral cabotegravir, no dosage adjustment of APRETUDE is necessary for individuals with mild or moderate hepatic impairment (Child-Pugh A or B). The effect of severe hepatic impairment (Child-Pugh C) on the pharmacokinetics of cabotegravir is unknown [see Clinical Pharmacology (12.3)].

10 OVERDOSAGE

There is no known specific treatment for overdose with APRETUDE. If overdose occurs, monitor the individual and apply standard supportive treatment as required as well as observation of the clinical status of the individual. As APRETUDE is highly bound to plasma proteins, it is unlikely that it will be significantly removed by dialysis. Consider the prolonged exposure to APRETUDE following an injection when assessing treatment needs and recovery [see Warnings and Precautions (5.5)].

11 DESCRIPTION

APRETUDE contains cabotegravir extended-release injectable suspension, an HIV INSTI.

The chemical name of cabotegravir is (3S,11aR)-N-[(2,4-difluorophenyl)methyl]-6-hydroxy-3-methyl-5,7-dioxo-2,3,5,7,11,11a-hexahydro[1,3]oxazolo[3,2-a]pyrido[1,2-d]pyrazine-8-carboxamide. The empirical formula is C19H17F2N3O5 and the molecular weight is 405.35 g/mol. It has the following structural formula:

Cabotegravir extended-release injectable suspension is a white to light pink free-flowing suspension for intramuscular injection in a sterile single-dose vial. Each vial contains 3 mL of the following: cabotegravir 200 mg/mL and the inactive ingredients mannitol (35 mg/mL), polyethylene glycol (PEG) 3350 (20 mg/mL), polysorbate 20 (20 mg/mL), and Water for Injection.

The vial stoppers are not made with natural rubber latex.

12 CLINICAL PHARMACOLOGY

12.1 Mechanism of Action

Cabotegravir is an HIV-1 antiretroviral drug [see Microbiology (12.4)] in a long-acting formulation.

12.2 Pharmacodynamics

Cardiac Electrophysiology

At a dose of cabotegravir 150 mg orally every 12 hours (10 times the recommended total daily oral lead‑in dosage of APRETUDE), the QT interval is not prolonged to any clinically relevant extent. Administration of 3 doses of cabotegravir 150 mg orally every 12 hours resulted in a geometric mean Cmax approximately 2.8- and 5.6-fold above the geometric mean steady-state Cmax associated with the recommended 30-mg dose of oral cabotegravir and the recommended 600-mg dose given every 2 months of cabotegravir extended-release injectable suspension, respectively.

12.3 Pharmacokinetics

Absorption, Distribution, and Elimination

The pharmacokinetic properties of cabotegravir are provided in Table 9. The multiple-dose pharmacokinetic parameters are provided in Table 10. For the pharmacokinetic properties of oral cabotegravir, refer to the full prescribing information for VOCABRIA (cabotegravir).

Table 9. Pharmacokinetic Properties of Cabotegravir
Absorptiona
Tmax (days), median | 7
Distribution
% Bound to human plasma proteins | >99.8
Blood-to-plasma ratio | 0.52
CSF-to-plasma concentration ratio (median [range])b | 0.003
 | (0.002 to 0.004)
Elimination
t1/2 (weeks), meanc | 5.6 to 11.5
Metabolism
Metabolic pathways | UGT1A1
 | UGT1A9 (minor)
Excretion
Major route of elimination | Metabolism
% of dose excreted as total ^14C (unchanged drug) in urined | 27 (0)
% of dose excreted as total ^14C (unchanged drug) in fecesd | 59 (47)
CSF = Cerebrospinal fluid.
a When taken orally with a high-fat meal versus fasted, the AUC(0-inf) (geometric mean ratio [90% CI] of cabotegravir are 1.14 [1.02, 1.28]).
b The clinical relevance of CSF-to-plasma concentration ratios is unknown. Concentrations were measured at steady-state 1 week after intramuscular administration of cabotegravir extended-release injectable suspensions given monthly or every 2 months.
c Elimination half-life driven by slow absorption rate from the intramuscular injection site.
d Dosing in mass balance studies: single-dose oral administration of [^14C] cabotegravir.

Table 10. Pharmacokinetic Parameters following Once-Daily Oral Cabotegravir and following Initiation and Every-2-Month Continuation Intramuscular Injections of APRETUDE
Dosing Phase | Dosage Regimen | Geometric Mean (5th, 95th Percentile)a
Dosing Phase | Dosage Regimen | AUC(0-tau)b (mcg•h/mL) | Cmax (mcg/mL) | Ctaub (mcg/mL)
Oral lead-inc | 30 mg | 145 | 8.0 | 4.6
 | once daily | (93.5, 224) | (5.3, 11.9) | (2.8, 7.5)
Initial injectiond | 600 mg IM | 1,591 | 8.0 | 1.5
 | initial dose | (714; 3,245) | (5.3, 11.9) | (0.65, 2.9)
Every-2-month injectione | 600 mg IM | 3,764 | 4.0 | 1.6
 | every 2 months | (2,431; 5,857) | (2.3, 6.8) | (0.8, 3.0)
IM = Intramuscular.
a Pharmacokinetic parameter values were based on individual post-hoc estimates from cabotegravir population pharmacokinetic models for patients in Phase 3 treatment studies of HIV treatment.
b tau is dosing interval: 24 hours for oral administration, 1 month for the initial injection, and 2 months for every 2 months for intramuscular injections of extended-release injectable suspension.
c Oral lead-in pharmacokinetic parameter values represent steady state.
d Initial injection Cmax values primarily reflect oral dosing because the initial injection was administered on the same day as the last oral dose; however, AUC(0-tau) and the Ctau values reflect the initial injection. When administered without oral lead-in to recipients with HIV-1 (n = 110), the observed cabotegravir geometric mean (5th, 95th percentile) Cmax (1-week post‑initial injection) was 1.89 mcg/mL (0.438, 5.69) and Ctau was 1.43 mcg/mL (0.403, 3.90).
e Pharmacokinetic parameter values represent steady state.

Specific Populations

No clinically significant differences in the pharmacokinetics of cabotegravir were observed based on age, sex, race/ethnicity, BMI, or UGT1A1 polymorphisms. There are no data available for the use of cabotegravir in participants with hepatitis B virus and hepatitis C virus co-infection in PrEP studies.

Renal Impairment: With oral cabotegravir, no clinically significant differences in the pharmacokinetics of cabotegravir are expected in individuals with mild, moderate, or severe renal impairment. Cabotegravir has not been studied in participants with end-stage renal disease not on dialysis. As cabotegravir is >99% protein bound, dialysis is not expected to alter exposures of cabotegravir [see Use in Specific Populations (8.6)].

Hepatic Impairment: No clinically significant differences in the pharmacokinetics of cabotegravir are expected in mild to moderate (Child-Pugh A or B) hepatic impairment. The effect of severe hepatic impairment (Child-Pugh C) on the pharmacokinetics of cabotegravir has not been studied [see Use in Specific Populations (8.7)].

Gender: Population pharmacokinetic analyses revealed no clinically relevant effect of gender on the exposure of cabotegravir. In addition, no clinically relevant differences in plasma cabotegravir concentrations were observed in PrEP studies by gender, including in cisgender men and transgender women (+/- hormone use). Therefore, no dose adjustment is necessary based on gender.

Geriatrics: No dose adjustment is required in elderly individuals. There are limited data available on the use of cabotegravir in individuals aged 65 years and older. In general, caution should be exercised in administration of cabotegravir in elderly individuals, reflecting greater frequency of decreased hepatic, renal, or cardiac function and of concomitant disease or other drug therapy [see Use in Specific Populations (8.5)].

Pediatrics: Population pharmacokinetic analyses revealed no clinically relevant differences in exposure between adolescent participants and adult participants with and without HIV-1 from the cabotegravir development program; therefore, no dosage adjustment is needed for adolescents weighing ≥35 kg (Table 11).

Table 11. Pharmacokinetic Parameters following Once-Daily Oral Cabotegravir and following Initiation and Every-2-Month Continuation Intramuscular Injections of APRETUDE in Adolescent Participants Aged 12 to Younger than 18 Years (≥35 kg)
Dosing Phase | Dosage Regimen | Geometric Mean (5th, 95th Percentile)a
Dosing Phase | Dosage Regimen | AUC(0-tau)b; (mcg•h/mL) | Cmax; (mcg/mL) | Ctaub; (mcg/mL)
Oral lead-inc | 30 mg | 203 | 10.7 | 6.43
 | once daily | (136, 320) | (7.36, 16.6) | (4.15, 10.5)
Initial injectiond | 600 mg IM | 2,085 | 10.8 | 1.88
 | initial dose | (1,056; 4,259) | (7.42, 16.6) | (0.801, 3.71)
Every-2-month injectione | 600 mg IM | 5,184 | 5.10 | 2.54
 | every 2 months | (3,511; 7,677) | (3.06, 8.24) | (1.25, 4.19)
IM = intramuscular.
a Pharmacokinetic parameter values were based on individual post-hoc estimates from population pharmacokinetic models in both adolescents with HIV-1 (n = 147) weighing 35.2 to 98.5 kg and adolescents without HIV-1 (n = 62) weighing 39.9 to 167 kg.
b tau is dosing interval: 24 hours for oral administration, 1 month for the initial injection, and 2 months for every 2 months for intramuscular injections of extended-release injectable suspension.
c Oral lead-in pharmacokinetic parameter values represent steady state.
d Initial injection Cmax values primarily reflect oral dosing because the initial injection was administered on the same day as the last oral dose; however, the AUC(0-tau) and Ctau values reflect the initial injection.
e Pharmacokinetic parameter values represent steady state.

Drug Interaction Studies

Cabotegravir is not a clinically relevant inhibitor of the following enzymes and transporters: cytochrome P450 (CYP)1A2, 2A6, 2B6, 2C8, 2C9, 2C19, 2D6, and 3A4; UGT1A1, 1A3, 1A4, 1A6, 1A9, 2B4, 2B7, 2B15, and 2B17; P-glycoprotein (P‑gp); breast cancer resistance protein (BCRP); bile salt export pump (BSEP); organic cation transporter (OCT)1, OCT2; organic anion transporter polypeptide (OATP)1B1, OATP1B3; multidrug and toxin extrusion transporter (MATE) 1, MATE 2-K; and multidrug resistance protein (MRP)2 or MRP4.

In vitro, cabotegravir inhibited renal OAT1 (IC50 = 0.81 microM) and OAT3 (IC50 = 0.41 microM). Based on physiologically based pharmacokinetic (PBPK) modeling, cabotegravir may increase the AUC of OAT1/3 substrates up to approximately 80%.

In vitro, cabotegravir did not induce CYP1A2, CYP2B6, or CYP3A4.

‎Simulations using PBPK modeling show that no clinically significant interaction is expected during coadministration of cabotegravir with drugs that inhibit UGT1A1.

In vitro, cabotegravir was not a substrate of OATP1B1, OATP1B3, OATP2B1, or OCT1.

Cabotegravir is a substrate of P-gp and BCRP in vitro; however, because of its high permeability, no alteration in cabotegravir absorption is expected with coadministration of P-gp or BCRP inhibitors.

Drug interaction studies were not conducted with injectable cabotegravir. Drug interaction studies with oral cabotegravir are summarized in Tables 12 and 13.

Table 12. Effect of Coadministered Drugs on the Pharmacokinetics of Cabotegravir
Coadministered Drug(s); and Dose(s) | Dose of Cabotegravir | n | Geometric Mean Ratio (90% CI) of Cabotegravir Pharmacokinetic Parameters with/without Coadministered Drugs; No Effect = 1.00
Coadministered Drug(s); and Dose(s) | Dose of Cabotegravir | n | Cmax | AUC | Ctau or C24
Etravirine | 30 mg | 12 | 1.04 | 1.01 | 1.00
200 mg twice daily | once daily |  | (0.99, 1.09) | (0.96, 1.06) | (0.94, 1.06)
Rifabutin | 30 mg | 12 | 0.83 | 0.77 | 0.74
300 mg once daily | once daily |  | (0.76, 0.90) | (0.74, 0.83) | (0.70, 0.78)
Rifampin | 30-mg | 15 | 0.94 | 0.41 | 0.50
600 mg once daily | single dose |  | (0.87, 1.02) | (0.36, 0.46) | (0.44, 0.57)
Rilpivirine | 30 mg | 11 | 1.05 | 1.12 | 1.14
25 mg once daily | once daily |  | (0.96, 1.15) | (1.05, 1.19) | (1.04, 1.24)
n = Maximum number of participants with data, CI = Confidence Interval.

Table 13. Effect of Cabotegravir on the Pharmacokinetics of Coadministered Drugs
Coadministered Drug(s); and Dose(s) | Dose of Cabotegravir | n | Geometric Mean Ratio (90% CI) of Pharmacokinetic Parameters of Coadministered Drug with/without Cabotegravir; No Effect = 1.00
Coadministered Drug(s); and Dose(s) | Dose of Cabotegravir | n | Cmax | AUC | Ctau or C24
Ethinyl estradiol | 30 mg | 19 | 0.92 | 1.02 | 1.00
0.03 mg once daily | once daily |  | (0.83, 1.03) | (0.97, 1.08) | (0.92, 1.10)
Levonorgestrel | 30 mg | 19 | 1.05 | 1.12 | 1.07
0.15 mg once daily | once daily |  | (0.96, 1.15) | (1.07, 1.18) | (1.01, 1.15)
Midazolam | 30 mg | 12 | 1.09 | 1.10 | NA
3 mg | once daily |  | (0.94, 1.26) | (0.95, 1.26)
Rilpivirine | 30 mg | 11 | 0.96 | 0.99 | 0.92
25 mg once daily | once daily |  | (0.85, 1.09) | (0.89, 1.09) | (0.79, 1.07)
n = Maximum number of participants with data, CI = Confidence Interval; NA = Not available.

12.4 Microbiology

Mechanism of Action

Cabotegravir inhibits HIV integrase by binding to the integrase active site and blocking the strand transfer step of retroviral deoxyribonucleic acid (DNA) integration that is essential for the HIV replication cycle. The mean 50% inhibitory concentration (IC50) value of cabotegravir in a strand transfer assay using purified recombinant HIV-1 integrase was 3.0 nM.

Antiviral Activity in Cell Culture

Cabotegravir exhibited antiviral activity against laboratory strains of HIV-1 (subtype B, n = 4) with mean 50 percent effective concentration (EC50) values of 0.22 to 1.7 nM in peripheral blood mononuclear cells (PBMCs) and 293 cells. Cabotegravir demonstrated antiviral activity in PBMCs against a panel of 24 HIV-1 clinical isolates (3 in each of group M subtypes A, B, C, D, E, F, and G and 3 in group O) with a median EC50 value of 0.19 nM (range: 0.02 to 1.06 nM, n = 24). The median EC50 value against subtype B clinical isolates was 0.05 nM (range: 0.02 to 0.50 nM, n = 3). Against clinical HIV-2 isolates, the median EC50 value was 0.12 nM (range: 0.10 to 0.14 nM, n = 3).

In cell culture, cabotegravir was not antagonistic in combination with the non-nucleoside reverse transcriptase inhibitor (NNRTI) rilpivirine, or the nucleoside reverse transcriptase inhibitors (NRTIs) FTC, lamivudine (3TC), or TDF.

Resistance

Cell Culture: Cabotegravir-resistant viruses were selected during passage of HIV-1 strain IIIB in MT-2 cells in the presence of cabotegravir. Amino acid substitutions in integrase that emerged and conferred decreased susceptibility to cabotegravir included Q146L (fold change: 1.3 to 4.6), S153Y (fold change: 2.8 to 8.4), and I162M (fold change: 2.8). The integrase substitution T124A also emerged alone (fold change: 1.1 to 7.4 in cabotegravir susceptibility), in combination with S153Y (fold change: 3.6 to 6.6 in cabotegravir susceptibility) or I162M (2.8-fold change in cabotegravir susceptibility). Cell culture passage of virus harboring integrase substitutions Q148H, Q148K, or Q148R selected for additional substitutions (C56S, V72I, L74M, V75A, T122N, E138K, G140S, G149A, and M154I), with substituted viruses having reduced susceptibility to cabotegravir of 2.0- to 410-fold change. The combinations of E138K+Q148K and V72I+E138K+Q148K conferred the greatest reductions of 53- to 260‑fold change and 410‑fold change, respectively.

Clinical Trials: There were 12 incident infections and 4 prevalent infections among participants in the APRETUDE arm of HPTN 083. Genotypic data were generated for viruses from 13 of these 16 participants (4 participants with prevalent infections and 9 participants with incident infections) and phenotypic data were generated for 3 of these viruses. INSTI resistance-associated substitutions were detected in 5 viruses from participants who achieved target plasma concentrations of cabotegravir (≥0.65 mcg/mL [1.6 μM]) and included R263K (2-fold less susceptible to cabotegravir), E138A+Q148R (6-fold less susceptible to cabotegravir), E138K+Q148K, G140A+Q148R (13-fold less susceptible to cabotegravir), and L74I+E138E/K+G140G/S+Q148R+E157Q.

There were 3 incident infections and 1 prevalent infection among participants in the APRETUDE arm of HPTN 084. All 3 incident infections occurred during periods with cabotegravir exposures below the target concentration. No variants expressing INSTI resistance-associated substitutions were detected.

Cross-Resistance

Cross-resistance has been observed among INSTIs. Cabotegravir had reduced susceptibility (>5-fold change) to recombinant HIV-1 strain NL432 viruses harboring the following integrase amino acid substitutions: G118R, Q148K, Q148R, T66K+L74M, E92Q+N155H, E138A+Q148R, E138K+Q148K/R, G140C+Q148R, G140S+Q148H/K/R, Y143H+N155H, and Q148R+N155H (range: 5.1- to 81-fold). The substitutions E138K+Q148K and Q148R+N155H conferred the greatest reductions in susceptibility of 81- and 61-fold, respectively.

Virologic failure isolates from cabotegravir plus rilpivirine treatment in FLAIR, ATLAS, and ATLAS-2M exhibited cross-resistance to INSTIs and NNRTIs. All confirmed virologic isolates with genotypic evidence of cabotegravir resistance had cross-resistance to elvitegravir and raltegravir but retained phenotypic susceptibility to dolutegravir and when tested bictegravir.

Viruses harboring E138A+Q148R or G140A+Q148R with reduced susceptibility to cabotegravir were isolated from participants using APRETUDE in HPTN 083. These viruses remained susceptible to bictegravir and dolutegravir but had cross-resistance to elvitegravir and raltegravir.

13 NONCLINICAL TOXICOLOGY

13.1 Carcinogenesis, Mutagenesis, Impairment of Fertility

Carcinogenesis

Two-year carcinogenicity studies in mice and rats were conducted with cabotegravir. In mice, no drug-related increases in tumor incidence were observed at cabotegravir exposures (AUC) up to approximately 8 times (males) and 7 times (females) higher than those in humans at the RHD. In rats, no drug-related increases in tumor incidence were observed at cabotegravir exposures up to approximately 26 times higher than those in humans at the RHD.

Mutagenesis

Cabotegravir was not genotoxic in the bacterial reverse mutation assay, mouse lymphoma assay, or in the in vivo rodent micronucleus assay.

Impairment of Fertility

In rats, no effects on fertility were observed at cabotegravir exposures (AUC) >20 times (male) and 28 times (female) the exposure in humans at the RHD.

14 CLINICAL STUDIES

14.1 Clinical Trials in Adults for HIV-1 Pre-Exposure Prophylaxis

The safety and efficacy of APRETUDE to reduce the risk of acquiring HIV-1 infection were evaluated in 2 randomized, double-blind, controlled, multinational trials, HPTN 083 in men and transgender women without HIV-1 who have sex with men and have evidence of high-risk behavior for HIV-1 infection and HPTN 084 in cisgender women without HIV-1 at risk of acquiring HIV-1.

Participants randomized to receive APRETUDE initiated oral lead-in dosing with 1 oral cabotegravir 30-mg tablet and a placebo daily for up to 5 weeks, followed by APRETUDE 600‑mg (3-mL) intramuscular injection at months 1 and 2 and every 2 months thereafter and a daily placebo tablet. Participants randomized to receive TRUVADA initiated oral TRUVADA (TDF 300 mg/FTC 200 mg) and placebo daily for up to 5 weeks, followed by oral TRUVADA daily and placebo intramuscular injection at months 1 and 2 and every 2 months thereafter.

Trial 201738 (HPTN 083 [NCT02720094])

In HPTN 083, a non-inferiority study, 4,566 cisgender men and transgender women who have sex with men were randomized 1:1 and received either APRETUDE (n = 2,281) or TRUVADA (n = 2,285) as blinded study medication up to Week 153.

At baseline, the median age of participants was 26 years, 12% were transgender women, 72% were non-White, and 67% were younger than 30 years.

The primary endpoint was the rate of incident HIV-1 infections among participants randomized to daily oral cabotegravir and intramuscular injections of APRETUDE every 2 months compared with daily oral TRUVADA (corrected for early stopping). The primary analysis demonstrated the superiority of APRETUDE compared with TRUVADA with a 66% reduction in the risk of acquiring HIV-1 infection, hazard ratio (95% CI) 0.34 (0.18, 0.62); further testing revealed 1 of the infections on APRETUDE to be prevalent then yielding a 69% reduction in the risk of HIV-1 incident infection relative to TRUVADA (Table 14).

Table 14. HIV-1 Infection Results During Randomized Phase in HPTN 083: Extended Retrospective Virologic Testing with Readjudicated Endpointsa
 | APRETUDE; (N = 2,278) | TRUVADA; (N = 2,281) | Superiority P Value
Person-years | 3,211 | 3,193
HIV-1 infections (incidence rate per 100 person-years) | 12b (0.37) | 39 (1.22)
Hazard ratio (95% CI) | 0.31 (0.16, 0.58) |  | 0.0003
a mITT from Supplemental Virology Report.
b Following the primary analysis, extended retrospective virologic testing was performed to better characterize the timing of HIV-1 infections. As a result, 1 of the 13 HIV-1 incident infections in participants receiving APRETUDE was determined to be a prevalent infection. The original hazard ratio (95% CI) from the primary analysis is 0.34 (0.18, 0.62).

Figure 1. Cumulative Incidence of HIV-1 Infections in HPTN 083

Results from all subgroup analyses were consistent with the overall protective effect. A lower rate of incident HIV‑1 infections was observed for participants randomized to APRETUDE compared with participants randomized to TRUVADA (Table 15).

Table 15. Incident of HIV-1 Infections by Subgroup in HPTN 083: Extended Retrospective Virologic Testing with Readjudicated Endpointsa
Subgroup | APRETUDE Incidence per 100 Person-Years | APRETUDE; Person-Years | TRUVADA; Incidence per 100 Person-Years | TRUVADA; Person-Years | Hazard Ratio; (95% CI)
Age
<30 years | 0.47 | 2,110 | 1.66 | 1,987 | 0.29
 |  |  |  |  | (0.15, 0.59)
≥30 years | 0.18 | 1,101 | 0.50 | 1,206 | 0.39
 |  |  |  |  | (0.08, 1.84)
Gender
MSMb | 0.35 | 2,836 | 1.14 | 2,803 | 0.32
 |  |  |  |  | (0.16, 0.64)
TGWc | 0.54 | 371 | 1.80 | 389 | 0.34
 |  |  |  |  | (0.08, 1.56)
Race (US)
Black | 0.58 | 691 | 2.28 | 703 | 0.26
 |  |  |  |  | (0.09, 0.76)
Non-Black | 0.00 | 836 | 0.50 | 801 | 0.11
 |  |  |  |  | (0.00, 2.80)
Region
US | 0.26 | 1,528 | 1.33 | 1,504 | 0.21
 |  |  |  |  | (0.07, 0.60)
Latin America | 0.49 | 1,020 | 1.09 | 1,011 | 0.47
 |  |  |  |  | (0.17, 1.35)
Asia | 0.35 | 570 | 1.03 | 581 | 0.39
 |  |  |  |  | (0.08, 1.82)
Africa | 1.08 | 93 | 2.07 | 97 | 0.63
 |  |  |  |  | (0.06, 6.50)
a mITT from Supplemental Virology Report.
b Cisgender men who have sex with men.
c Transgender women who have sex with men.

Trial 201739 (HPTN 084 [NCT03164564])

In HPTN 084, a superiority study, 3,224 cisgender women were randomized 1:1 and received either APRETUDE (n = 1,614) or TRUVADA (n = 1,610) as blinded study medication up to Week 153.

At baseline, the median age of participants was 25 years, >99% were non-White, >99% were cisgender women, and 49% were <25 years of age.

The primary endpoint was the rate of incident HIV-1 infections among participants randomized to oral cabotegravir and injections of APRETUDE compared with oral TRUVADA (corrected for early stopping). The primary analysis demonstrated the superiority of APRETUDE compared with TRUVADA with an 88% reduction in the risk of acquiring incident HIV-1 infection, hazard ratio (95% CI) 0.12 (0.05, 0.31); further testing revealed 1 of the infections on APRETUDE to be prevalent then yielding a 90% reduction in the risk of HIV-1 incident infection relative to TRUVADA (Table 16).

Table 16. HIV-1 Infection Results during Randomized Phase in HPTN 084: Extended Retrospective Virologic Testing with Readjudicated Endpointsa
 | APRETUDE; (N = 1,613) | TRUVADA; (N = 1,610) | Superiority; P Value
Person-years | 1,960 | 1,946
HIV-1 incident infections (incidence rate per 100 person-years) | 3b (0.15) | 36 (1.85)
Hazard ratio (95% CI) | 0.10 (0.04, 0.27) |  | <0.0001
a mITT from Supplemental Virology Report.
b Following the primary analysis, extended retrospective virologic testing was performed to better characterize the timing of HIV-1 infections. As a result, 1 of the 4 HIV-1 incident infections in participants receiving APRETUDE was determined to be a prevalent infection. The original hazard ratio (95% CI) from the primary analysis is 0.12 (0.05, 0.31).

Figure 2. Cumulative Incidence of HIV-1 Infections in HPTN 084

Results from pre-planned subgroup analyses were consistent with the overall protective effect. A lower rate of incident HIV-1 infections was observed for participants randomized to APRETUDE compared with participants randomized to TRUVADA (Table 17).

Table 17. Incident of HIV-1 Infections by Subgroup in HPTN 084: Extended Retrospective Virologic Testing with Readjudicated Endpointsa
Subgroup | APRETUDE Incidence; per 100 Person-Years | APRETUDE Person-Years | TRUVADA Incidence; per 100 Person-Years | TRUVADA Person-Years | Hazard Ratio; (95% CI)
Age
<25 years | 0.23 | 868 | 2.34 | 853 | 0.12
 |  |  |  |  | (0.03, 0.46)
≥25 years | 0.09 | 1,093 | 1.46 | 1,093 | 0.09
 |  |  |  |  | (0.02, 0.49)
Body Mass Index
<30 | 0.22 | 1,385 | 1.88 | 1,435 | 0.12
 |  |  |  |  | (0.04, 0.38)
≥30 | 0.00 | 575 | 1.76 | 511 | 0.04
 |  |  |  |  | (0.00, 0.93)
a mITT from Supplemental Virology Report.

16 HOW SUPPLIED/STORAGE AND HANDLING

How Supplied

APRETUDE is supplied in a kit containing one 600-mg/3-mL single-dose (200-mg/mL) vial of cabotegravir extended-release injectable suspension, 1 syringe, 1 vial adapter, and 1 needle for intramuscular injection (23 gauge, 1½ inch) (NDC 49702-264-23). The vial stopper is not made with natural rubber latex.

Storage and Handling

Store APRETUDE at 2°C to 25°C (36°F to 77°F) in the original carton until ready to use. Exposure up to 30°C permitted. Do not freeze. Do not mix with any other product or diluent.

If the pack has been stored in the refrigerator, the vial should be brought to room temperature prior to administration (not to exceed 30°C [86°F]).

Once the suspension has been drawn into the syringe, the injection should be administered as soon as possible, but may remain in the syringe for up to 2 hours. The filled syringes should not be placed in the refrigerator. If the medicine remains in the syringe for more than 2 hours, the filled syringe and needle must be discarded [see Dosage and Administration (2.7)].

17 PATIENT COUNSELING INFORMATION

Advise the individual to read the FDA-approved patient labeling (Patient Information).

Important Information for Individuals without HIV-1 Taking APRETUDE for HIV-1 Pre‑Exposure Prophylaxis

Advise individuals without HIV-1 about the following [see Warnings and Precautions (5.1)]:

- APRETUDE should be used for PrEP as part of an overall HIV-1 infection prevention strategy, including adherence to the administration schedule and safer sex practices, including condoms, to reduce the risk of STIs.
- APRETUDE is not always effective in preventing HIV-1 acquisition [see Clinical Studies (14.1)]. The time from initiation of APRETUDE for HIV-1 PrEP to maximal protection against HIV-1 infection is unknown.
- Counsel individuals on the use of other prevention measures (e.g., knowledge of partner HIV-1 status, testing for STIs condom use). Inform individuals about and support their efforts in reducing sexual risk behavior.
- APRETUDE should be used to reduce the risk of acquiring HIV-1 only in individuals confirmed to be HIV-1 negative [see Contraindications (4), Warnings and Precautions (5.1)]. HIV-1 resistance substitutions may emerge in individuals with undiagnosed HIV-1 infection who are taking only APRETUDE, because APRETUDE alone does not constitute a complete regimen for HIV-1 treatment; therefore, care should be taken to minimize the risk of initiating or continuing APRETUDE before confirming the individual is HIV-1 negative.
- If recent (<1 month) exposures to HIV-1 are suspected or clinical symptoms consistent with acute HIV-1 infection are present, use a test approved or cleared by the FDA as an aid in the diagnosis of acute or primary HIV-1 infection.
- When using APRETUDE for HIV-1 PrEP, HIV-1 testing should be repeated prior to each injection of APRETUDE, and upon diagnosis of any other STIs.
- If an HIV-1 test indicates possible HIV-1 infection, or if symptoms consistent with acute HIV-1 infection develop following an exposure event, additional HIV testing to determine HIV status is needed. If an individual has confirmed HIV-1 infection, then the individual must be transitioned to a complete HIV-1 treatment regimen.
- Some individuals, such as adolescents, may benefit from frequent visits and counseling to support adherence.

Potential Risk of Resistance with APRETUDE

Advise individuals there is a potential risk of developing resistance to APRETUDE if HIV-1 is acquired either before or while taking APRETUDE or following discontinuation of APRETUDE [see Warnings and Precautions (5.2)].

To minimize this, it is essential that individuals are clinically reassessed for risk of HIV-1 acquisition and tested frequently to confirm HIV-1 negative status. Advise individuals who are confirmed to have with HIV-1 infection to consult with their healthcare professional, as HIV-1 treatment must be initiated [see Warnings and Precautions (5.2)].

Inform individuals that alternative forms of PrEP should be considered following discontinuation of APRETUDE for those at continuing risk of HIV-1 acquisition and initiated within 2 months of the final injection of APRETUDE [see Warnings and Precautions (5.2)].

Long-Acting Properties of APRETUDE

Advise individuals that APRETUDE is an extended-release injectable that may be systemically present for 12 months or longer and consideration should be taken regarding the prolonged release characteristics when APRETUDE is discontinued [see Warnings and Precautions (5.3), Drug Interactions (7)].

Adherence to APRETUDE

Counsel individuals about the importance of continued medication adherence and scheduled visits to help reduce the risk of acquiring HIV-1 infection and development of resistance [see Dosage and Administration (2.3), Warnings and Precautions (5.1)].

Hypersensitivity Reactions

Advise individuals to immediately contact their healthcare provider if they develop a rash. Instruct individuals to immediately stop taking APRETUDE and seek medical attention if they develop a rash associated with any of the following symptoms as it may be a sign of a more serious reaction such as Stevens-Johnson syndrome (SJS)/toxic epidermal necrolysis (TEN): fever; generally ill feeling; extreme tiredness; muscle or joint aches; blisters; oral blisters or lesions; eye inflammation; facial swelling; swelling of the eyes, lips, tongue, or mouth; difficulty breathing; and/or signs and symptoms of liver problems (e.g., yellowing of the skin or whites of the eyes; dark or tea‑colored urine; pale-colored stools or bowel movements; nausea; vomiting; loss of appetite; or pain, aching, or sensitivity on the right side below the ribs). Advise individuals that if hypersensitivity occurs, they will be closely monitored, laboratory tests will be ordered, and appropriate therapy will be initiated [see Warnings and Precautions (5.4)].

Hepatotoxicity

Inform individuals that hepatotoxicity has been reported with cabotegravir [see Warnings and Precautions (5.5), Adverse Reactions (6.1)]. Inform individuals that clinical and laboratory monitoring should be considered and APRETUDE should be discontinued if hepatoxicity is confirmed [see Warnings and Precautions (5.5)].

Depressive Disorders

Inform individuals that depressive disorders (including depression, depressed mood, major depression, persistent depressive disorder, suicidal ideation, suicide attempt) have been reported with APRETUDE [see Adverse Reactions (6.1)]. Advise individuals to seek prompt medical evaluation if they experience depressive symptoms [see Warnings and Precautions (5.6)].

Drug Interactions

Inform individuals that APRETUDE may interact with other drugs and may reduce exposure of APRETUDE; therefore, advise individuals to report to their healthcare provider the use of any other prescription or nonprescription medication [see Contraindications (4), Warnings and Precautions (5.7), Drug Interactions (7.2, 7.3)].

Missed Dose

Inform individuals that APRETUDE can remain in the body for up to 12 months or longer after receiving their last injection. Advise individuals that they should contact their healthcare provider if they miss or plan to miss a scheduled monthly injection visit and that oral dosing may be used to replace up to 2 consecutive monthly injections. Advise individuals that if they discontinue use of APRETUDE, they will need to take other medicines for HIV-1 PrEP [see Dosage and Administration (2.3, 2.6), Warnings and Precautions (5.3)].

Pregnancy Registry

Inform individuals that there is an antiretroviral pregnancy registry to monitor fetal outcomes in those exposed to APRETUDE during pregnancy. Individuals who are of reproductive potential should be informed of the long duration of exposure of APRETUDE and that there is very limited clinical experience in human pregnancy [see Warnings and Precautions (5.3), Use in Specific Populations (8.1)].

Lactation

Inform individuals that due to the potential for adverse reactions and residual concentrations in the systemic circulation for up to 12 months or longer after discontinuing injections of APRETUDE, it is recommended that mothers breastfeed only if the expected benefit justifies the potential risk to the infant. The benefits and risks of APRETUDE while breastfeeding should be evaluated, including the risk of HIV-1 acquisition due to medication nonadherence and subsequent mother to child transmission. Instruct mothers not to breastfeed if acute HIV-1 infection is suspected because of the risk of passing the HIV-1 virus to the baby [see Use in Specific Populations (8.2)].

APRETUDE, CABENUVA, and VOCABRIA are trademarks owned by or licensed to the ViiV Healthcare group of companies.

The other brand listed is a trademark owned by or licensed to its respective owner and is not a trademark owned by or licensed to the ViiV Healthcare group of companies. The maker of this brand is not affiliated with and does not endorse the ViiV Healthcare group of companies or its products.

Manufactured for:

ViiV Healthcare
Durham, NC 27701

©2025 ViiV Healthcare group of companies or its licensor.

APR:5PI

PATIENT INFORMATION

APRETUDE [AP-reh-tood]

(cabotegravir extended-release injectable suspension)

for intramuscular use

What is the most important information I should know about APRETUDE?

Important information for people who receive APRETUDE to help reduce their risk of getting human immunodeficiency virus-1 (HIV-1) infection, also called pre-exposure prophylaxis or “PrEP”:

Before receiving APRETUDE to reduce your risk of getting HIV-1:

- You must be HIV-1 negative to start APRETUDE. You must get tested to make sure that you do not already have HIV-1 infection.
- Do not receive APRETUDE for HIV-1 PrEP unless you are confirmed to be HIV-1 negative.
- Some HIV-1 tests can miss HIV-1 infection in a person who has recently become infected. If you have flu-like symptoms, you could have recently become infected with HIV-1. Tell your healthcare provider if you had a flu-like illness within the last month before starting APRETUDE or at any time while receiving APRETUDE. Symptoms of new HIV-1 infection include:

○ tiredness
○ joint or muscle aches
○ sore throat
○ rash
○ enlarged lymph nodes in the neck or groin

○ fever
○ headache
○ vomiting or diarrhea
○ night sweats

While you are receiving APRETUDE for HIV-1 PrEP:

- APRETUDE does not prevent other sexually transmitted infections. Practice safer sex by using a latex or polyurethane condom to reduce the risk of getting sexually transmitted infections.
- You must stay HIV-1 negative to keep receiving APRETUDE for HIV-1 PrEP.
  - Know your HIV-1 status and the HIV-1 status of your partners.
  - Ask your partners with HIV-1 if they are taking anti-HIV-1 medicines and have an undetectable viral load. An undetectable viral load is when the amount of virus in the blood is too low to be measured in a lab test. To maintain an undetectable viral load, your partners must keep taking HIV-1 medicine as prescribed. Your risk of getting HIV-1 is lower if your partners with HIV-1 are taking effective treatment.
  - Get tested for HIV-1 with each APRETUDE injection or when your healthcare provider tells you. You should not miss any HIV-1 tests. If you become HIV-1–infected and continue receiving APRETUDE because you do not know you are HIV-1–infected, the HIV-1 infection may become harder to treat.
  - Get tested for other sexually transmitted infections such as syphilis, chlamydia, and gonorrhea. These infections make it easier for HIV-1 to infect you.
  - If you think you were exposed to HIV-1, tell your healthcare provider right away. They may want to do more tests to be sure you are still HIV-1 negative.
  - Get information and support to help reduce sexual risk behaviors.
  - Do not miss any injections of APRETUDE. Missing injections increases your risk of getting HIV-1 infection.
  - If you do become HIV-1 positive, you will need to take other medicines to treat HIV-1. APRETUDE is not approved for treatment of HIV-1.

If you have HIV-1 and receive only APRETUDE, over time your HIV-1 may become harder to treat.

What is APRETUDE?

APRETUDE is a prescription medicine used for HIV-1 PrEP to reduce the risk of getting HIV-1 infection in adults and adolescents who weigh at least 77 pounds (at least 35 kg).

HIV-1 is the virus that causes acquired immune deficiency syndrome (AIDS).

It is not known if APRETUDE is safe and effective in children younger than 12 years of age or weighing less than 77 pounds (less than 35 kg).

Do not receive APRETUDE if you:

- already have HIV-1 infection. If you are HIV-1 positive, you will need to take other medicines to treat HIV-1. APRETUDE is not approved for treatment of HIV-1.
- do not know your HIV-1 infection status. You may already be HIV-1 positive. You need to take other medicines to treat HIV-1. APRETUDE can only help reduce your risk of getting HIV-1 infection before you are infected.
- have ever had an allergic reaction to cabotegravir
- are taking any of the following medicines:

○ carbamazepine
○ oxcarbazepine
○ phenobarbital

○ phenytoin
○ rifampin
○ rifapentine

Before receiving APRETUDE, tell your healthcare provider about all your medical conditions, including if you:

- have ever had a skin rash or an allergic reaction to medicines that contain cabotegravir.
- have or have had liver problems.
- have ever had mental health problems.
- are pregnant or plan to become pregnant. It is not known if APRETUDE will harm your unborn baby. APRETUDE can remain in your body for up to 12 months or longer after the last injection. Tell your healthcare provider if you become pregnant while or after receiving APRETUDE.
  Pregnancy Registry. There is a pregnancy registry for those who receive APRETUDE during pregnancy. The purpose of this registry is to collect information about the health of you and your baby. Talk to your healthcare provider about how you can take part in this registry.
- are breastfeeding or plan to breastfeed. APRETUDE may pass into your breast milk. Talk with your healthcare provider about the best way to feed your baby while or after receiving APRETUDE.

Tell your healthcare provider about all the medicines you take, including prescription and over-the-counter medicines, vitamins, and herbal supplements.

Some medicines may interact with APRETUDE. Keep a list of your medicines and show it to your healthcare provider and pharmacist when you get a new medicine.

You can ask your healthcare provider or pharmacist for a list of medicines that interact with APRETUDE.

Do not start a new medicine without telling your healthcare provider. Your healthcare provider can tell you if it is safe to receive APRETUDE with other medicines.

How will I receive APRETUDE?

- APRETUDE will be given to you as an injection by your healthcare provider.
- APRETUDE is initially given as an injection into the muscle of your buttock 1 time every month for the first 2 months, then as an injection 1 time every 2 months.
- Before receiving your first injection dose of APRETUDE, your healthcare provider may have you take 1 VOCABRIA (cabotegravir) tablet 1 time a day for 1 month (at least 28 days). This will allow your healthcare provider to assess how well you will tolerate cabotegravir.
- APRETUDE is a long-acting medicine and may stay in your body for 12 months or longer after your last injection.
- Stay under the care of a healthcare provider while receiving APRETUDE. It is important that you receive APRETUDE as scheduled.
- If you miss or plan to miss a scheduled injection of APRETUDE by more than 7 days, call your healthcare provider right away to discuss your PrEP options.
- If you stop receiving APRETUDE, talk to your healthcare provider about other options to reduce the risk of getting HIV-1 infection.

What are the possible side effects of APRETUDE?

APRETUDE may cause serious side effects including:

- Allergic reactions. Call your healthcare provider right away if you develop a rash with APRETUDE. Stop receiving APRETUDE and get medical help right away if you develop a rash with any of the following signs or symptoms:

○ fever
○ generally ill feeling
○ tiredness
○ muscle or joint aches
○ trouble breathing

○ blisters or sores in mouth
○ blisters
○ redness or swelling of the eyes
○ swelling of the mouth, face, lips, or tongue

- Liver problems. Liver problems have happened in people with or without a history of liver problems or other risk factors. Your healthcare provider may do blood tests to check your liver function.
  Call your healthcare provider right away if you develop any of the following signs or symptoms of liver problems:

○ your skin or the white part of your eyes turns yellow (jaundice)

○ dark or “tea-colored” urine
○ light-colored stools (bowel movements)
○ nausea or vomiting

○ loss of appetite

○ pain, aching, or tenderness on the right side of your stomach area

○ itching

- Depression or mood changes. Call your healthcare provider or get medical help right away if you develop any of the following symptoms:
  ○ feeling sad or hopeless
  ○ feeling anxious or restless
  ○ have thoughts of hurting yourself (suicide) or have tried to hurt yourself

The most common side effects of APRETUDE include:

- pain, tenderness, hardened mass or lump, swelling, bruising, redness, itching, warmth, loss of sensation at the injection site, abscess, and discoloration
- diarrhea
- headache
- fever
- tiredness
- sleep problems
- nausea

- dizziness
- passing gas
- stomach pain
- vomiting
- muscle pain
- rash
- loss of appetite
- drowsiness
- back pain
- upper respiratory infection

These are not all the possible side effects of APRETUDE.

Call your doctor for medical advice about side effects. You may report side effects to FDA at 1-800-FDA-1088.

General information about the safe and effective use of APRETUDE.

Medicines are sometimes prescribed for purposes other than those listed in a Patient Information leaflet. You can ask your pharmacist or healthcare provider for information about APRETUDE that is written for health professionals.

What are the ingredients in APRETUDE?

Active ingredient: cabotegravir

Inactive ingredients: mannitol, polyethylene glycol (PEG) 3350, polysorbate 20, and Water for Injection.

Manufactured for:

ViiV Healthcare

Durham, NC 27701

APRETUDE and VOCABRIA are trademarks owned by or licensed to the ViiV Healthcare group of companies.

©2025 ViiV Healthcare group of companies or its licensor.

APR:5PIL

For more information, go to www.apretude.com or call 1-877-844-8872.

This Patient Information has been approved by the U.S. Food and Drug Administration. Revised: 4/2025

INSTRUCTIONS FOR USE

Overview:

A complete dose of APRETUDE requires 1 injection: 600-mg (3 mL) of cabotegravir.

APRETUDE is a suspension that does not need further dilution or reconstitution. Carefully follow these instructions when preparing the suspension for injection to avoid leakage.

APRETUDE is for gluteal intramuscular use only.

Note: The ventrogluteal site is recommended.

Storage information

Store at 2°C to 25°C (36°F to 77°F). Exposure up to 30°C (86°F) permitted.

Do not freeze.

Prior to administration:

- If the pack has been stored in the refrigerator, the vial should be brought to room temperature prior to administration (not to exceed 30°C [86°F]).
- Once APRETUDE has been drawn into the syringe, the medicine can remain in the syringe for up to 2 hours before injection. The filled syringe should not be placed in the refrigerator. If the medicine remains in the syringe for more than 2 hours, the filled syringe and needle must be discarded.

Your pack contains:

- 1 vial of APRETUDE
- 1 vial adapter
- 1 syringe
- 1 injection needle (23 gauge, 1½ inch)

Consider the individual’s build and use medical judgment to select an appropriate injection needle length.

You will also need:

- Non-sterile gloves
- 2 alcohol wipes
- 2 gauze pads
- A suitable sharps container

Preparation:

1. Inspect the vial.

Figure A

- Check that the expiration date has not passed. See Figure A.
- Inspect the vial immediately. If you can see foreign matter, do not use the product.
Note: The vial has a brown tint to the glass.
Do not use if the expiration date has passed.
- If the pack has been stored in the refrigerator, allow the medication to come to room temperature.

2. Shake the vial vigorously.

Figure B

- Hold the vial firmly, and vigorously shake for a full 10 seconds. See Figure B.

3. Inspect suspension.

Figure C

- Invert the vial and confirm the suspension is uniform. It should look uniform. See Figure C.
- If the suspension is not uniform, shake the vial again.
- It is also normal to see small air bubbles.

4. Remove the vial cap.

Figure D

- Remove the cap from the vial. See Figure D.
- Wipe the rubber stopper with an alcohol wipe.
Do not allow anything to touch the rubber stopper after wiping it.

5. Peel open the vial adapter.

Figure E

- Peel off the paper backing from the vial adapter packaging. See Figure E.
Note: Do not remove the adapter from its packaging for the next step. The adapter will not fall out when its packaging is turned upside down.

6. Place vial on flat surface and attach the vial adapter.

Figure F

- Ensure the vial is upright and on a flat surface. See Figure F.
- Press the vial adapter straight down onto the vial, as shown.
- The vial adapter should click securely into place.

7. Lift off the packaging.

Figure G

- Lift off the vial adapter packaging, as shown. See Figure G.

8. Prepare the syringe.

Figure H

- Remove the syringe from its packaging.
- Draw 1 mL of air into the syringe. This will make it easier to draw up the medicine later. See Figure H.

9. Attach the syringe.

Figure I

- Hold the vial adapter and vial firmly, as shown.
- Screw the syringe firmly onto the vial adapter. See Figure I.

10. Press the plunger.

Figure J

- Press the plunger all the way down to push the air into the vial. See Figure J.

11. Slowly draw up the dose.

Figure K

- Invert the syringe and vial and slowly withdraw as much of the medicine as possible into the syringe. There may be more medicine than the dose amount. See Figure K.
Note: Keep the syringe upright to avoid leakage.

12. Unscrew the syringe.

Figure L

- Hold the syringe plunger firmly in place as shown to prevent leakage. It is normal to feel some back pressure.
- Unscrew the syringe from the vial adapter, holding the vial adapter as shown. See Figure L.
Note: Check that the suspension looks uniform and milky white.

13. Attach the needle.

Figure M

- Peel open the needle packaging part way to expose the needle base.
- Keeping the syringe upright, firmly twist the syringe onto the needle.
- Remove the needle packaging from the needle. See Figure M.

Injection:

14. Prepare the injection site.

Figure N

APRETUDE must be administered to a gluteal site. See Figure N.
Select from the following areas for the injection:

- Ventrogluteal, as shown (recommended)
- Dorsogluteal, not shown (upper outer quadrant)
Note: For gluteal intramuscular use only.
  Do not inject intravenously.

15. Remove the cap.

Figure O

- Fold the needle guard away from the needle. See Figure O.
- Pull off the injection needle cap.

16. Remove extra liquid from the syringe.

Figure P

- Hold the syringe with the needle pointing up. Press the plunger to the 3 mL dosing mark to remove extra liquid and any air bubbles. See Figure P.
Note: Clean the injection site with an alcohol wipe. Allow the skin to air dry before continuing.

17. Stretch the skin.

Figure Q

Use the z-track injection technique to minimize medicine leakage from the injection site.

- Firmly drag the skin covering the injection site, displacing it by about an inch (2.5 cm). See Figure Q.
- Keep it held in this position for the injection.

18. Insert the needle.

Figure R

- Insert the needle to its full depth, or deep enough to reach the muscle. See Figure R.

19. Inject the dose of medicine.

Figure S

- Still holding the skin stretched – slowly press the plunger all the way down. See Figure S.
- Ensure the syringe is empty.
- Withdraw the needle and release the stretched skin immediately.

20. Assess the injection site.

Figure T

- Apply pressure to the injection site using a gauze pad. See Figure T.
- A small bandage may be used if bleeding occurs.
Do not massage the area.

21. Make the needle safe.

Figure U

- Fold the needle guard over the needle. See Figure U.

Figure V

- Gently apply pressure using a hard surface to lock the needle guard in place.
- The needle guard will make a click when it locks. See Figure V.

After injection:

22. Dispose safely.

Figure W

- Dispose of used needle, syringe, vial, and vial adapter according to local health and safety laws. See Figure W.

Questions and Answers

1. If the pack has been stored in the refrigerator, is it safe to warm the vial up to room temperature more quickly?
  The vial should be brought to room temperature before you are ready to give the injection, but make sure the vial does not get above 30°C (86°F).
Do not use any heating methods, other than using the warmth of your hands.
2. How long can APRETUDE be left in the syringe?
  It is best to inject (room temperature) APRETUDE as soon as possible after drawing it up. However, APRETUDE can remain in the syringe for up to 2 hours before injection.
  If the medicine remains in the syringe for more than 2 hours, the filled syringe and needle must be discarded.
3. Why do I need to inject air into the vial?
  Injecting 1 mL of air into the vial makes it easier to draw up the medicine into the syringe. Without the air, some liquid may flow back into the vial unintentionally, leaving less medicine than intended in the syringe.
4. Why is the ventrogluteal administration approach recommended?
  The ventrogluteal approach into the gluteus medius muscle is recommended because it is located away from major nerves and blood vessels. A dorsogluteal approach into the gluteus maximus muscle is acceptable, if preferred by the healthcare professional. The injection should not be administered in any other site.

Manufactured for:

ViiV Healthcare

Durham, NC 27701

Trademarks are owned by or licensed to the ViiV Healthcare group of companies.

©2024 ViiV Healthcare group of companies or its licensor.

APR:5IFU

This Instructions for Use has been approved by the U.S. Food and Drug Administration. Revised: 9/2024

PACKAGE LABEL

Principal Display Panel

NDC 49702-264-23

Apretude

(cabotegravir extended-release injectable suspension)

600 mg/3 mL

(200 mg/mL)

Rx Only

For gluteal intramuscular use only.

Healthcare Professional Administration Only.

Contents:

1 Single-dose vial

1 Vial adapter

1 Syringe

1 Injection needle (23 gauge, 1 ½ inch)

Prescribing Information

Patient Information

Instructions for Use

Ensure vial adapter is used correctly.

ViiV Healthcare

600 mg/ 3 mL Kit

Made in Singapore and Belgium

Rev. 2/24

©2024 ViiV Healthcare group of companies or its licensor.

62000000092471

PACKAGE LABEL

Principal Display Panel

NDC 49702-280-63

Apretude

(cabotegravir extended-release injectable suspension)

600 mg/3 mL

(200 mg/mL)

Rx Only

Sample-Not for Sale

For gluteal intramuscular use only.

Healthcare Professional Administration Only.

Contents:

1 Single-dose vial

1 Vial adapter

1 Syringe

1 Injection needle (23 gauge, 1 ½ inch)

Prescribing Information

Patient Information

Instructions for Use

Ensure vial adapter is used correctly.

ViiV Healthcare

600 mg/ 3 mL Kit

Made in Singapore and Belgium

Rev. 5/24

©2024 ViiV Healthcare group of companies or its licensor.

62000000094179